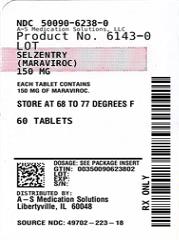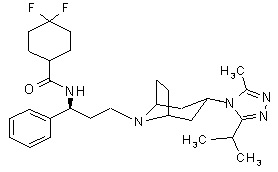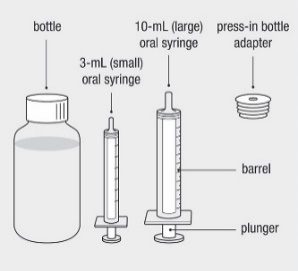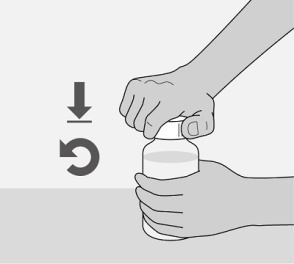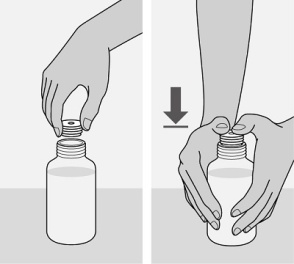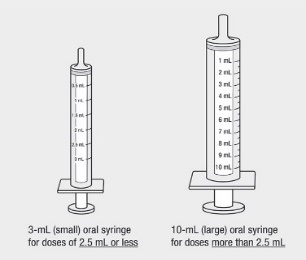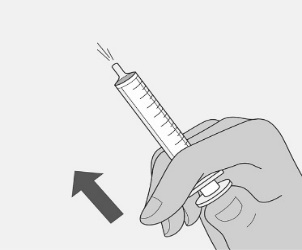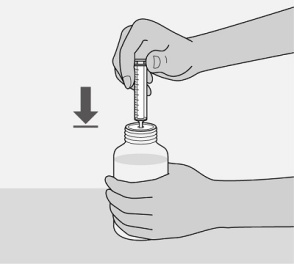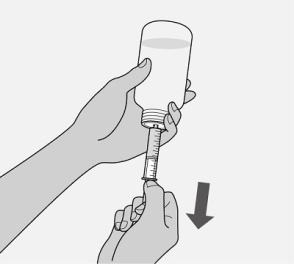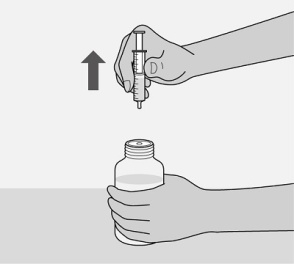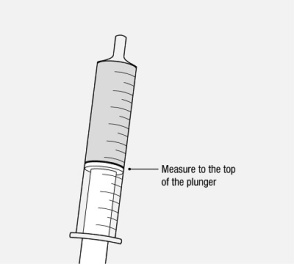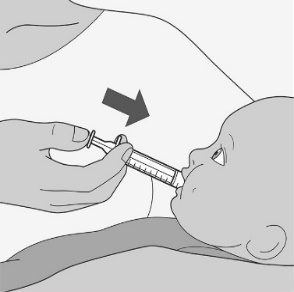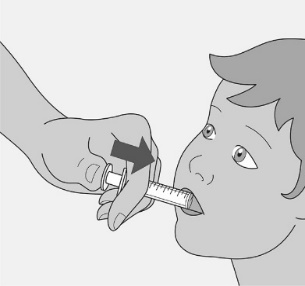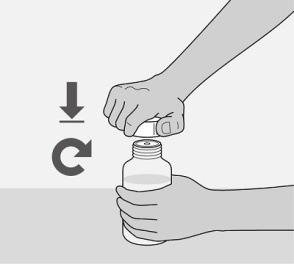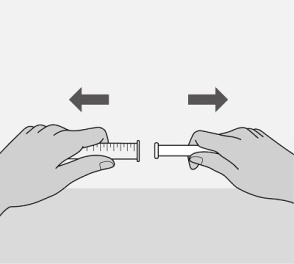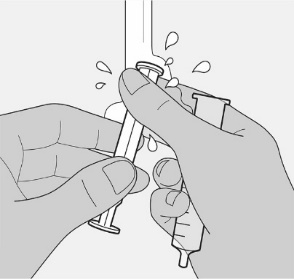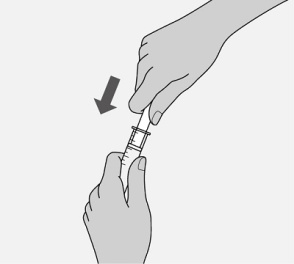 DRUG LABEL: SELZENTRY
NDC: 50090-6238 | Form: TABLET, FILM COATED
Manufacturer: A-S Medication Solutions
Category: prescription | Type: HUMAN PRESCRIPTION DRUG LABEL
Date: 20231110

ACTIVE INGREDIENTS: MARAVIROC 150 mg/1 1
INACTIVE INGREDIENTS: ANHYDROUS DIBASIC CALCIUM PHOSPHATE; MAGNESIUM STEARATE; MICROCRYSTALLINE CELLULOSE; SODIUM STARCH GLYCOLATE TYPE A POTATO; FD&C BLUE NO. 2; ALUMINUM OXIDE; HYDROGENATED SOYBEAN LECITHIN; POLYETHYLENE GLYCOL, UNSPECIFIED; POLYVINYL ALCOHOL, UNSPECIFIED; TALC; TITANIUM DIOXIDE

HIGHLIGHTS OF PRESCRIBING INFORMATION

These highlights do not include all the information needed to use SELZENTRY safely and effectively. See full prescribing information for SELZENTRY.
SELZENTRY (maraviroc) tablets, for oral use
SELZENTRY (maraviroc) oral solution
Initial U.S. Approval: 2007

WARNING: HEPATOTOXICITY

See full prescribing information for complete boxed warning.

- Hepatotoxicity has been reported which may be preceded by severe rash or other features of a systemic allergic reaction (e.g., fever, eosinophilia, or elevated IgE). (5.1)
- Immediately evaluate patients with signs or symptoms of hepatitis or allergic reaction. (5.1)

1 INDICATIONS AND USAGE

SELZENTRY is a CCR5 co-receptor antagonist indicated in combination with other antiretroviral agents for the treatment of only CCR5-tropic HIV-1 infection in adults and pediatric patients weighing at least 2 kg. (1)

Limitations of Use:

- Not recommended in patients with dual/mixed- or CXCR4-tropic HIV-1. (1)

2 DOSAGE AND ADMINISTRATION

- Prior to initiation of SELZENTRY for treatment of HIV-1 infection, test all patients for CCR5 tropism using a highly sensitive tropism assay. (2.1)
- SELZENTRY tablets and oral solution are taken twice daily by mouth and may be taken with or without food. SELZENTRY must be given in combination with other antiretroviral medications. (2.2)

Recommended Dosage in Adult Patients: (2.3)

Concomitant Medications | Dosage of SELZENTRY
When given with potent cytochrome P450 (CYP)3A inhibitors (with or without potent CYP3A inducers) including PIs (except tipranavir/ritonavir) (2.3, 7.1) | 150 mg; twice daily
With NRTIs, tipranavir/ritonavir, nevirapine, raltegravir, and other drugs that are not potent CYP3A inhibitors or CYP3A inducers (2.3, 7.1) | 300 mg; twice daily
With potent and moderate CYP3A inducers including efavirenz (without a potent CYP3A inhibitor) (2.3, 7.1) | 600 mg; twice daily

A more complete list of coadministered drugs is listed in Dosage and Administration. (2)

Recommended Dosage in Pediatric Patients Weighing at Least 2 kg: Administer twice daily. Dosage should be based on body weight (kg) and concomitant medications and should not exceed the recommended adult dose. (2.4)

Recommended Dosage in Patients with Renal Impairment: Dose adjustment may be necessary in adult patients with renal impairment. (2.5)

3 DOSAGE FORMS AND STRENGTHS

- Tablets: 25 mg, 75 mg, 150 mg and 300 mg. (3)
- Oral Solution: 20 mg per mL (3)

4 CONTRAINDICATIONS

SELZENTRY is contraindicated in patients with severe renal impairment or end-stage renal disease (ESRD) (creatinine clearance [CrCl] less than 30 mL per minute) who are concomitantly taking potent CYP3A inhibitors or inducers. (4)

5 WARNINGS AND PRECAUTIONS

- Hepatotoxicity accompanied by severe rash or systemic allergic reaction, including potentially life-threatening events, has been reported. Hepatic laboratory parameters including alanine aminotransferase (ALT), aspartate aminotransferase (AST), and bilirubin should be obtained prior to starting SELZENTRY and at other time points during treatment as clinically indicated. If rash or symptoms or signs of hepatitis or allergic reaction develop, hepatic laboratory parameters should be monitored and discontinuation of treatment should be considered. When administering SELZENTRY to patients with pre-existing liver dysfunction or who are co-infected with hepatitis B and/or C virus, additional monitoring may be warranted. (5.1)
- Severe and potentially life-threatening skin and hypersensitivity reactions have been reported in patients taking SELZENTRY. This includes cases of Stevens-Johnson syndrome, hypersensitivity reaction, and toxic epidermal necrolysis. Immediately discontinue SELZENTRY and other suspected agents if signs or symptoms of severe skin or hypersensitivity reactions develop and monitor clinical status, including liver aminotransferases, closely. (5.2)
- More cardiovascular events, including myocardial ischemia and/or infarction, were observed in treatment-experienced subjects who received SELZENTRY. Additional monitoring may be warranted. (5.3)
- If patients with severe renal impairment or ESRD receiving SELZENTRY (without concomitant CYP3A inducers or inhibitors) experience postural hypotension, the dose of SELZENTRY should be reduced from 300 mg twice daily to 150 mg twice daily. (5.3)

6 ADVERSE REACTIONS

- The most common adverse events in treatment-experienced adult subjects (greater than 8% incidence) which occurred at a higher frequency compared with placebo are upper respiratory tract infections, cough, pyrexia, rash, and dizziness. (6.1)
- The most common adverse events in treatment-naive adult subjects (greater than 8% incidence) which occurred at a higher frequency than the comparator arm are upper respiratory tract infections, bronchitis, flatulence, bloating and distention, upper respiratory tract signs and symptoms, and gastrointestinal atonic and hypomotility disorders. (6.1)
- The most common adverse reactions in treatment-experienced pediatric subjects (greater than or equal to 3% incidence) are vomiting, abdominal pain, diarrhea, nausea, and dizziness. (6.1)

To report SUSPECTED ADVERSE REACTIONS, contact ViiV Healthcare at 1-877-844-8872 or FDA at 1-800-FDA-1088 or www.fda.gov/medwatch.

7 DRUG INTERACTIONS

- Coadministration with CYP3A inhibitors, including protease inhibitors (except tipranavir/ritonavir), will increase the concentration of SELZENTRY. (7.1)
- Coadministration with CYP3A inducers, including efavirenz, may decrease the concentration of SELZENTRY. (7.1)
- Coadministration with St. John’s wort is not recommended. (7.1)

8 USE IN SPECIFIC POPULATIONS

- Lactation: Women infected with HIV should be instructed not to breastfeed due to the potential for HIV transmission. (8.2)

FULL PRESCRIBING INFORMATION

WARNING: HEPATOTOXICITY

Hepatotoxicity has been reported with use of SELZENTRY. Severe rash or evidence of a systemic allergic reaction (e.g., fever, eosinophilia, or elevated IgE) prior to the development of hepatotoxicity may occur. Patients with signs or symptoms of hepatitis or allergic reaction following use of SELZENTRY should be evaluated immediately [see Warnings and Precautions (5.1)].

1 INDICATIONS AND USAGE

SELZENTRY is indicated in combination with other antiretroviral agents for the treatment of only CCR5‑tropic human immunodeficiency virus type 1 (HIV‑1) infection in adult and pediatric patients weighing at least 2 kg.

Limitations of Use

- SELZENTRY is not recommended in patients with dual/mixed- or CXCR4-tropic HIV-1 [see Microbiology (12.4)].

2 DOSAGE AND ADMINISTRATION

2.1 Testing prior to Initiation of SELZENTRY

Prior to initiation of SELZENTRY for treatment of HIV-1 infection, test all patients for CCR5 tropism using a highly sensitive tropism assay. SELZENTRY is recommended for patients with only CCR5-tropic HIV-1 infection. Outgrowth of pre-existing low-level CXCR4- or dual/mixed-tropic HIV-1 not detected by tropism testing at screening has been associated with virologic failure on SELZENTRY [see Microbiology (12.4), Clinical Studies (14.1)].

Monitor patients for alanine aminotransferase (ALT), aspartate aminotransferase (AST), and bilirubin prior to initiation of SELZENTRY and at other time points during treatment as clinically indicated [see Warnings and Precautions (5.1)].

2.2 General Dosing Recommendations

- SELZENTRY tablets and oral solution are taken twice daily by mouth and may be taken with or without food.
- SELZENTRY must be given in combination with other antiretroviral medications.
- The recommended dosage of SELZENTRY differs based on concomitant medications due to drug interactions.

2.3 Recommended Dosage in Adult Patients with Normal Renal Function

Table 1 displays oral dosage of SELZENTRY based on different concomitant medications [see Drug Interactions (7.1)].

Table 1. Recommended Dosage in Adults
Concomitant Medications | Dosage of SELZENTRY
Potent cytochrome P450 (CYP)3A inhibitors (with or without a potent CYP3A inducer)a | 150 mg twice daily
Noninteracting concomitant medicationsb | 300 mg twice daily
Potent and moderate CYP3A inducers (without a potent CYP3A inhibitor)c | 600 mg twice daily
a Potent CYP3A inhibitors (with or without a potent CYP3A inducer) including: clarithromycin, cobicistat, elvitegravir/ritonavir, itraconazole, ketoconazole, nefazodone, protease inhibitors (except tipranavir/ritonavir), telithromycin.
b Noninteracting concomitant medications include all medications that are not potent CYP3A inhibitors or inducers such as: dolutegravir, enfuvirtide, nevirapine, all nucleoside reverse transcriptase inhibitors (NRTIs), raltegravir, and tipranavir/ritonavir.
c Potent and moderate CYP3A inducers (without a potent CYP3A inhibitor) including: carbamazepine, efavirenz, etravirine, phenobarbital, phenytoin, and rifampin.

2.4 Recommended Dosage in Pediatric Patients with Normal Renal Function

The recommended dosage of SELZENTRY should be based on body weight (kg) and should not exceed the recommended adult dose. The recommended dosage also differs based on concomitant medications due to drug interactions (Table 2 and Table 3) [see Drug Interactions (7.1), Use in Specific Populations (8.4)].

Before prescribing SELZENTRY tablets, assess children for the ability to swallow tablets. If a child is unable to reliably swallow SELZENTRY tablets, the oral solution formulation should be prescribed.

The recommended oral dosage of SELZENTRY tablets in pediatric patients aged 2 years and older weighing at least 10 kg is presented in Table 2.

Table 2. Recommended Dosage in Pediatric Patients Aged 2 Years and Older Weighing at Least 10 kg (Tablets)
Concomitant Medications | Dosage of SELZENTRY Based on Weight
Concomitant Medications | 10 kg to <14 kg | 14 kg to <20 kg | 20 kg to <30 kg | 30 kg to <40 kg | ≥40 kg
Potent CYP3A inhibitors (with or without a CYP3A inducer)a | 50 mg twice daily | 50 mg twice daily | 75 mg twice daily | 100 mg twice daily | 150 mg twice daily
Noninteracting concomitant medicationsb | 150 mg twice daily | 200 mg twice daily | 200 mg twice daily | 300 mg twice daily | 300 mg twice daily
Potent and moderate CYP3A inducers (without a potent CYP3A inhibitor)c | Not recommendedd
a Potent CYP3A inhibitors (with or without a CYP3A inducer) including: clarithromycin, cobicistat, elvitegravir/ritonavir, itraconazole, ketoconazole, nefazodone, protease inhibitors (except tipranavir/ritonavir), telithromycin.
b Noninteracting concomitant medications including all medications that are not potent CYP3A inhibitors or inducers such as: dolutegravir, enfuvirtide, nevirapine, all NRTIs, raltegravir, and tipranavir/ritonavir.
c Potent and moderate CYP3A inducers (without a potent CYP3A inhibitor) including: carbamazepine, efavirenz, etravirine, phenobarbital, phenytoin, and rifampin.
d Insufficient data are available to recommend use.

The recommended oral dosage of SELZENTRY oral solution in pediatric patients weighing at least 2 kg is presented in Table 3.

Table 3. Recommended Dosage in Pediatric Patients Weighing at Least 2 kg (Oral Solution)
Concomitant Medications | Dosage (Volume of Solution) of SELZENTRY Based on Weight
Concomitant Medications | 2 kg to <4 kg | 4 kg to <6 kg | 6 kg to; <10 kg | 10 kg to; <14 kg | 14 kg to <20 kg | 20 kg to <30 kg | 30 kg to <40 kg | ≥40 kg
Potent CYP3A inhibitors (with or without a CYP3A inducer)a | Not recommendedb |  |  | 50 mg (2.5 mL) twice daily | 50 mg (2.5 mL) twice daily | 80 mg (4 mL) twice daily | 100 mg (5 mL) twice daily | 150 mg (7.5 mL) twice daily
Noninteracting concomitant medicationsc | 30 mg (1.5 mL) twice daily | 40 mg (2 mL) twice daily | 100 mg (5 mL) twice daily | 150 mg (7.5 mL) twice daily | 200 mg (10 mL) twice daily | 200 mg (10 mL) twice daily | 300 mg (15 mL) twice daily | 300 mg (15 mL) twice daily
Potent and moderate CYP3A inducers (without a potent CYP3A inhibitor)d | Not recommendedb
a Potent CYP3A inhibitors (with or without a CYP3A inducer) including: clarithromycin, cobicistat, elvitegravir/ritonavir, itraconazole, ketoconazole, nefazodone, protease inhibitors (except tipranavir/ritonavir), telithromycin.
b Insufficient data are available to recommend use.
c Noninteracting concomitant medications including all medications that are not potent CYP3A inhibitors or inducers such as: dolutegravir, enfuvirtide, nevirapine, all NRTIs, raltegravir, and tipranavir/ritonavir.
d Potent and moderate CYP3A inducers (without a potent CYP3A inhibitor) including: carbamazepine, efavirenz, etravirine, phenobarbital, phenytoin, and rifampin.

Administer the oral solution using the included press-in bottle adapter and the appropriate oral dosing syringe: for doses of 2.5 mL or less, use the 3-mL syringe; for doses greater than 2.5 mL, use the 10-mL syringe.

Care should be taken when measuring neonate doses due to the small volumes of oral solution required.

2.5 Recommended Dosage in Patients with Renal Impairment

Adult Patients

Table 4 provides dosing recommendations for patients based on renal function and concomitant medications.

Table 4. Recommended Dosage in Adults Based on Renal Function
Concomitant Medications | Dosage of SELZENTRY Based on Renal Function
Concomitant Medications | Normal; (CrCl >80 mL/min) | Mild; (CrCl >50 and ≤80 mL/min) | Moderate; (CrCl ≥30 and ≤50 mL/min) | Severe; (CrCl <30 mL/min) | End-Stage Renal Disease on Regular Hemodialysis
Potent CYP3A inhibitors (with or without a CYP3A inducer)a | 150 mg twice daily | 150 mg twice daily | 150 mg twice daily | Contra-indicated | Contra-indicated
Noninteracting concomitant medicationsb | 300 mg twice daily | 300 mg twice daily | 300 mg twice daily | 300 mg twice daily | 300 mg twice dailyc
Potent and moderate CYP3A inducers (without a potent CYP3A inhibitor)d | 600 mg twice daily | 600 mg twice daily | 600 mg twice daily | Contra-indicated | Contra-indicated
CrCl = Creatinine clearance.
a Potent CYP3A inhibitors (with or without a CYP3A inducer) including: clarithromycin, cobicistat, elvitegravir/ritonavir, itraconazole, ketoconazole, nefazodone, protease inhibitors (except tipranavir/ritonavir), telithromycin.
b Noninteracting concomitant medications include all medications that are not potent CYP3A inhibitors or inducers such as: dolutegravir, enfuvirtide, nevirapine, all NRTIs, raltegravir, and tipranavir/ritonavir.
c Dosage of SELZENTRY should be reduced to 150 mg twice daily if there are any symptoms of postural hypotension [see Contraindications (4), Warnings and Precautions (5.3)].
d Potent and moderate CYP3A inducers (without a potent CYP3A inhibitor) including: carbamazepine, efavirenz, etravirine, phenobarbital, phenytoin, and rifampin.

Pediatric Patients

There are no data to recommend specific doses of SELZENTRY in pediatric patients with mild or moderate renal impairment [see Use in Specific Populations (8.6)]. Additionally, SELZENTRY is contraindicated for pediatric patients with severe renal impairment or end-stage renal disease (ESRD) on regular hemodialysis who are receiving potent CYP3A inhibitors or inducers [see Contraindications (4)].

3 DOSAGE FORMS AND STRENGTHS

Tablets:

- 25-mg blue, oval, film-coated tablets debossed with “MVC 25” on one side and plain on the other.
- 75-mg blue, oval, film-coated tablets debossed with “MVC 75” on one side and plain on the other.
- 150-mg blue, oval, film-coated tablets debossed with “MVC 150” on one side and plain on the other.
- 300-mg blue, oval, film-coated tablets debossed with “MVC 300” on one side and plain on the other.

Oral Solution:

- 20 mg per mL clear, colorless, strawberry-flavored oral solution.

4 CONTRAINDICATIONS

SELZENTRY is contraindicated in patients with severe renal impairment or ESRD (creatinine clearance [CrCl] less than 30 mL per minute) who are concomitantly taking potent CYP3A inhibitors or inducers [see Warnings and Precautions (5.3)].

5 WARNINGS AND PRECAUTIONS

5.1 Hepatotoxicity

Hepatotoxicity with allergic features including life-threatening events has been reported in clinical trials and postmarketing. Severe rash or evidence of systemic allergic reaction including drug-related rash with fever, eosinophilia, elevated IgE, or other systemic symptoms have been reported in conjunction with hepatotoxicity [see Warnings and Precautions (5.2)]. These events occurred approximately 1 month after starting treatment. Among reported cases of hepatitis, some were observed in the absence of allergic features or with no pre-existing hepatic disease.

Appropriate laboratory testing including ALT, AST, and bilirubin should be conducted prior to initiating therapy with SELZENTRY and at other time points during treatment as clinically indicated. Hepatic laboratory parameters should be obtained in any patient who develops rash, or signs or symptoms of hepatitis, or allergic reaction. Discontinuation of SELZENTRY should be considered in any patient with signs or symptoms of hepatitis, or with increased liver transaminases combined with rash or other systemic symptoms.

When administering SELZENTRY to patients with pre-existing liver dysfunction or who are co-infected with hepatitis B and/or C virus, additional monitoring may be warranted. The safety and efficacy of SELZENTRY have not been specifically studied in patients with significant underlying liver disorders.

5.2 Severe Skin and Hypersensitivity Reactions

Severe, potentially life-threatening skin and hypersensitivity reactions have been reported in patients taking SELZENTRY, in most cases concomitantly with other drugs associated with these reactions. These include cases of Stevens-Johnson syndrome (SJS), toxic epidermal necrolysis (TEN), and drug rash with eosinophilia and systemic symptoms (DRESS) [see Adverse Reactions (6.2)]. The cases were characterized by features including rash, constitutional findings, and sometimes organ dysfunction, including hepatic failure. Discontinue SELZENTRY and other suspected agents immediately if signs or symptoms of severe skin or hypersensitivity reactions develop (including, but not limited to, severe rash or rash accompanied by fever, malaise, muscle or joint aches, blisters, oral lesions, conjunctivitis, facial edema, lip swelling, eosinophilia). Delay in stopping treatment with SELZENTRY or other suspect drugs after the onset of rash may result in a life-threatening reaction. Clinical status, including liver aminotransferases, should be monitored and appropriate therapy initiated.

5.3 Cardiovascular Events

Eleven subjects (1.3%) who received SELZENTRY had cardiovascular events, including myocardial ischemia and/or infarction, during the Phase 3 trials in treatment‑experienced subjects (total exposure 609 patient‑years [300 on SELZENTRY once daily + 309 on SELZENTRY twice daily]), while no subjects who received placebo had such events (total exposure 111 patient‑years). These subjects generally had cardiac disease or cardiac risk factors prior to use of SELZENTRY, and the relative contribution of SELZENTRY to these events is not known.

In the Phase 2b/3 trial in treatment‑naive adult subjects, 3 subjects (0.8%) who received SELZENTRY had events related to ischemic heart disease and 5 subjects (1.4%) who received efavirenz had such events (total exposure 506 and 508 patient‑years for SELZENTRY and efavirenz, respectively).

When SELZENTRY was administered to healthy volunteers at doses higher than the recommended dose, symptomatic postural hypotension was seen at a greater frequency than in placebo. However, when SELZENTRY was given at the recommended dose in HIV-1–infected adult subjects in Phase 3 trials, postural hypotension was seen at a rate similar to placebo (approximately 0.5%).

Patients with cardiovascular comorbidities, risk factors for postural hypotension, or receiving concomitant medication known to lower blood pressure, could be at increased risk of cardiovascular adverse events triggered by postural hypotension. Additional monitoring may be warranted.

Postural Hypotension in Patients with Renal Impairment

An increased risk of postural hypotension may occur in patients with severe renal insufficiency or in those with ESRD due to increased maraviroc exposure in some patients. SELZENTRY should be used in patients with severe renal impairment or ESRD only if they are not receiving a concomitant potent CYP3A inhibitor or inducer. However, the use of SELZENTRY in these patients should only be considered when no alternative treatment options are available. If adult patients with severe renal impairment or ESRD experience any symptoms of postural hypotension while taking 300 mg twice daily, the dose should be reduced to 150 mg twice daily [see Dosage and Administration (2.5)].

5.4 Immune Reconstitution Syndrome

Immune reconstitution syndrome has been reported in patients treated with combination antiretroviral therapy, including SELZENTRY. During the initial phase of combination antiretroviral treatment, patients whose immune systems respond may develop an inflammatory response to indolent or residual opportunistic infections (such as infection with Mycobacterium avium infection, cytomegalovirus, Pneumocystis jirovecii pneumonia [PCP], tuberculosis, or reactivation of Herpes simplex and Herpes zoster), which may necessitate further evaluation and treatment.

Autoimmune disorders (such as Graves’ disease, polymyositis, and Guillain-Barré syndrome) have also been reported to occur in the setting of immune reconstitution; however, the time to onset is more variable, and can occur many months after initiation of treatment.

5.5 Potential Risk of Infection

SELZENTRY antagonizes the CCR5 co-receptor located on some immune cells, and therefore could potentially increase the risk of developing infections. The overall incidence and severity of infection, as well as AIDS-defining category C infections, were comparable in the treatment groups during the Phase 3 adult treatment‑experienced trials of SELZENTRY. While there was a higher rate of certain upper respiratory tract infections reported in the treatment arm receiving SELZENTRY compared with placebo (23% versus 13%), there was a lower rate of pneumonia (2% versus 5%) reported in subjects receiving SELZENTRY. A higher incidence of Herpes virus infections (11 per 100 patient‑years) was also reported in the treatment arm receiving SELZENTRY when adjusted for exposure compared with placebo (8 per 100 patient‑years).

In the Phase 2b/3 trial in treatment‑naive adult subjects, the incidence of AIDS-defining Category C events when adjusted for exposure was 1.8 for SELZENTRY compared with 2.4 for efavirenz per 100 patient‑years of exposure.

Patients should be monitored closely for evidence of infections while receiving SELZENTRY.

5.6 Potential Risk of Malignancy

While no increase in malignancy has been observed with SELZENTRY, due to this drug’s mechanism of action, it could affect immune surveillance and lead to an increased risk of malignancy.

The exposure-adjusted rate for malignancies per 100 patient‑years of exposure in adult treatment‑experienced trials was 4.6 for SELZENTRY compared with 9.3 on placebo. In treatment‑naive adult subjects, the rates were 1.0 and 2.4 per 100 patient‑years of exposure for SELZENTRY and efavirenz, respectively.

Long-term follow-up is needed to more fully assess this risk.

6 ADVERSE REACTIONS

The following adverse reactions are discussed in other sections of the labeling:

- Hepatotoxicity [see Boxed Warning, Warnings and Precautions (5.1)]
- Severe Skin and Hypersensitivity Reactions [see Warnings and Precautions (5.2)]
- Cardiovascular Events [see Warnings and Precautions (5.3)]

6.1 Clinical Trials Experience

Because clinical trials are conducted under widely varying conditions, adverse reaction rates observed in the clinical trials of a drug cannot be directly compared with rates in the clinical trials of another drug and may not reflect the rates observed in practice.

Clinical Trials Experience in Adult Subjects

Treatment‑Experienced Subjects: The safety profile of SELZENTRY is primarily based on 840 HIV-1–infected subjects who received at least 1 dose of SELZENTRY during two Phase 3 trials. A total of 426 of these subjects received the indicated twice‑daily dosing regimen.

Assessment of treatment‑emergent adverse events is based on the pooled data from 2 trials in subjects with CCR5-tropic HIV‑1 (A4001027 and A4001028). The median duration of therapy with SELZENTRY for subjects in these trials was 48 weeks, with the total exposure on SELZENTRY twice daily at 309 patient‑years versus 111 patient‑years on placebo each administered with optimized background therapy (OBT). The population was 89% male and 84% white, with mean age of 46 years (range: 17 to 75 years). Subjects received dose equivalents of 300 mg maraviroc once or twice daily.

The most common adverse events reported with twice‑daily therapy with SELZENTRY with frequency rates higher than placebo, regardless of causality, were upper respiratory tract infections, cough, pyrexia, rash, and dizziness. In these 2 trials, the rate of discontinuation due to adverse events was 5% for subjects who received SELZENTRY twice daily + OBT as well as those who received placebo + OBT. Most of the adverse events reported were judged to be mild to moderate in severity. The data described below occurred with twice‑daily dosing of SELZENTRY.

The total numbers of subjects reporting infections were 233 (55%) and 84 (40%) in the group receiving SELZENTRY twice daily and the placebo group, respectively. Correcting for the longer duration of exposure on SELZENTRY compared with placebo, the exposure‑adjusted frequency (rate per 100 subject‑years) of these events was 133 for both SELZENTRY twice daily and placebo.

Dizziness or postural dizziness occurred in 8% of subjects on either SELZENTRY or placebo, with 2 subjects (0.5%) on SELZENTRY permanently discontinuing therapy (1 due to syncope, 1 due to orthostatic hypotension) versus 1 subject on placebo (0.5%) permanently discontinuing therapy due to dizziness.

Treatment-emergent adverse events, regardless of causality, from Trials A4001027 and A4001028 are summarized in Table 5. Selected events occurring at greater than or equal to 2% of subjects and at a numerically higher rate in subjects treated with SELZENTRY are included; events that occurred at the same or higher rate on placebo are not displayed.

Table 5. Selected Treatment-Emergent Adverse Events (All Causality) ≥2% on SELZENTRY (and at a Higher Rate Compared with Placebo) in Trials A4001027 and A4001028 (Pooled Analysis, 48 Weeks)
 | SELZENTRY; Twice Dailya |  | Placebo
Body System/; Adverse Event | (n = 426); % | Exposure-Adjusted Rate; (per 100 pt-yrs); PYE = 309b | (n = 209); % | Exposure-Adjusted Rate; (per 100 pt-yrs); PYE = 111b
Eye Disorders
Conjunctivitis | 2 | 3 | 1 | 3
Ocular infections, inflammations, and associated manifestations | 2 | 3 | 1 | 2
Gastrointestinal Disorders
Constipation | 6 | 9 | 3 | 6
General Disorders and Administration Site Conditions
Pyrexia | 13 | 20 | 9 | 17
Pain and discomfort | 4 | 5 | 3 | 5
Infections and Infestations
Upper respiratory tract infection | 23 | 37 | 13 | 27
Herpes infection | 8 | 11 | 4 | 8
Sinusitis | 7 | 10 | 3 | 6
Bronchitis | 7 | 9 | 5 | 9
Folliculitis | 4 | 5 | 2 | 4
Anogenital warts | 2 | 3 | 1 | 3
Influenza | 2 | 3 | 0.5 | 1
Otitis media | 2 | 3 | 0.5 | 1
Metabolism and Nutrition Disorders
Appetite disorders | 8 | 11 | 7 | 13
Musculoskeletal and Connective Tissue Disorders
Joint-related signs and symptoms | 7 | 10 | 3 | 5
Muscle pains | 3 | 4 | 0.5 | 1
Neoplasms Benign, Malignant, and Unspecified
Skin neoplasms benign | 3 | 4 | 1 | 3
Nervous System Disorders
Dizziness/postural dizziness | 9 | 13 | 8 | 17
Paresthesias and dysesthesias | 5 | 7 | 3 | 6
Sensory abnormalities | 4 | 6 | 1 | 3
Disturbances in consciousness | 4 | 5 | 3 | 6
Peripheral neuropathies | 4 | 5 | 3 | 6
Psychiatric Disorders
Disturbances in initiating and maintaining sleep | 8 | 11 | 5 | 10
Depressive disorders | 4 | 6 | 3 | 5
Anxiety symptoms | 4 | 5 | 3 | 7
Renal and Urinary Disorders
Bladder and urethral symptoms | 5 | 7 | 1 | 3
Urinary tract signs and symptoms | 3 | 4 | 1 | 3
Respiratory, Thoracic, and Mediastinal Disorders
Coughing and associated symptoms | 14 | 21 | 5 | 10
Upper respiratory tract signs and symptoms | 6 | 9 | 3 | 6
Nasal congestion and inflammations | 4 | 6 | 3 | 5
Breathing abnormalities | 4 | 5 | 2 | 5
Paranasal sinus disorders | 3 | 4 | 0.5 | 1
Skin and Subcutaneous Tissue Disorders
Rash | 11 | 16 | 5 | 11
Apocrine and eccrine gland disorders | 5 | 7 | 4 | 7.5
Pruritus | 4 | 5 | 2 | 4
Lipodystrophies | 3 | 5 | 0.5 | 1
Erythema | 2 | 3 | 1 | 2
Vascular Disorders
Vascular hypertensive disorders | 3 | 4 | 2 | 4
a 300-mg dose equivalent.
b PYE = Patient-years of exposure.

Laboratory Abnormalities: Table 6 shows the treatment-emergent Grade 3-4 laboratory abnormalities that occurred in greater than 2% of subjects receiving SELZENTRY.

Table 6. Maximum Shift in Laboratory Test Values (without Regard to Baseline) ≥2% of Grade 3-4 Abnormalities (ACTG Criteria) in Trials A4001027 and A4001028 (Pooled Analysis, 48 Weeks)
Laboratory Parameter Preferred Term | Limit | SELZENTRY; Twice Daily + OBT; (n = 421)a; % | Placebo + OBT; (n = 207)a; %
Aspartate aminotransferase | >5.0 x ULN | 4.8 | 2.9
Alanine aminotransferase | >5.0 x ULN | 2.6 | 3.4
Total bilirubin | >2.5 x ULN | 5.5 | 5.3
Amylase | >2.0 x ULN | 5.7 | 5.8
Lipase | >2.0 x ULN | 4.9 | 6.3
Absolute neutrophil count | <750/mm^3 | 4.3 | 2.4
ULN = Upper limit of normal; OBT = Optimized background therapy.
a Percentages based on total subjects evaluated for each laboratory parameter.

Treatment‑Naive Subjects: Treatment-Emergent Adverse Events: Treatment-emergent adverse events, regardless of causality, from Trial A4001026, a double-blind, comparative, controlled trial in which 721 treatment-naive subjects received SELZENTRY 300 mg twice daily (n = 360) or efavirenz 600 mg once daily (n = 361) in combination with lamivudine/zidovudine (COMBIVIR) for 96 weeks, are summarized in Table 7. Selected events occurring in greater than or equal to 2% of subjects and at a numerically higher rate in subjects treated with SELZENTRY are included; events that occurred at the same or higher rate on efavirenz are not displayed.

Table 7. Selected Treatment-Emergent Adverse Events (All Causality) ≥2% on SELZENTRY (and at a Higher Rate Compared with Efavirenz) in Trial A4001026 (96 Weeks)
Body System/; Adverse Event | SELZENTRY 300 mg Twice Daily +; Lamivudine/Zidovudine; (n = 360); % | Efavirenz 600 mg Once Daily +; Lamivudine/Zidovudine; (n = 361); %
Blood and Lymphatic System Disorders
Anemias NEC | 8 | 5
Neutropenias | 4 | 3
Ear and Labyrinth Disorders
Ear disorders NEC | 3 | 2
Gastrointestinal Disorders
Flatulence, bloating, and distention | 10 | 7
Gastrointestinal atonic and hypomotility disorders NEC | 9 | 5
Gastrointestinal signs and symptoms NEC | 3 | 2
General Disorders and Administration Site Conditions
Body temperature perception | 3 | 1
Infections and Infestations
Upper respiratory tract infection | 32 | 30
Bronchitis | 13 | 9
Herpes infection | 7 | 6
Bacterial infections NEC | 6 | 3
Herpes zoster/varicella | 5 | 4
Tinea infections | 4 | 3
Lower respiratory tract and lung infections | 3 | 2
Neisseria infections | 3 | 0
Viral infections NEC | 3 | 2
Musculoskeletal and Connective Tissue Disorders
Joint-related signs and symptoms | 6 | 5
Nervous System Disorders
Paresthesias and dysesthesias | 4 | 3
Memory loss (excluding dementia) | 3 | 1
Renal and Urinary Disorders
Bladder and urethral symptoms | 4 | 3
Reproductive System and Breast Disorders
Erection and ejaculation conditions and disorders | 3 | 2
Respiratory, Thoracic, and Mediastinal Disorders
Upper respiratory tract signs and symptoms | 9 | 5
Skin and Subcutaneous Disorders
Nail and nail bed conditions (excluding infections and infestations) | 6 | 2
Lipodystrophies | 4 | 3
Acnes | 3 | 2
Alopecias | 2 | 1

Laboratory Abnormalities:

Table 8. Maximum Shift in Laboratory Test Values (without Regard to Baseline) ≥2% of Grade 3-4 Abnormalities (ACTG Criteria) in Trial A4001026 (96 Weeks)
Laboratory Parameter Preferred Term | Limit | SELZENTRY; 300 mg Twice Daily +; Lamivudine/Zidovudine (n = 353)a; % | Efavirenz; 600 mg Once Daily+; Lamivudine/Zidovudine (n = 350)a; %
Aspartate aminotransferase | >5.0 x ULN | 4.0 | 4.0
Alanine aminotransferase | >5.0 x ULN | 3.9 | 4.0
Creatine kinase | >10.0 x ULN | 3.9 | 4.8
Amylase | >2.0 x ULN | 4.3 | 6.0
Absolute neutrophil count | <750/mm^3 | 5.7 | 4.9
Hemoglobin | <7.0 g/dL | 2.9 | 2.3
ULN = Upper limit of normal.
a n = Total number of subjects evaluable for laboratory abnormalities.
Percentages based on total subjects evaluated for each laboratory parameter. If the same subject in a given treatment group had greater than 1 occurrence of the same abnormality, only the most severe is counted.

Less Common Adverse Events in Clinical Trials: The following adverse events occurred in less than 2% of subjects treated with SELZENTRY or at a rate similar to the comparator. These events have been included because of their seriousness and either increased frequency on SELZENTRY or are potential risks due to the mechanism of action. Events attributed to the subjects’ underlying HIV-1 infection are not listed.

Blood and Lymphatic System: Marrow depression and hypoplastic anemia.

Cardiac Disorders: Unstable angina, acute cardiac failure, coronary artery disease, coronary artery occlusion, myocardial infarction, myocardial ischemia.

Hepatobiliary Disorders: Hepatic cirrhosis, hepatic failure, cholestatic jaundice, portal vein thrombosis, jaundice.

Infections and Infestations: Endocarditis, infective myositis, viral meningitis, pneumonia, treponema infections, septic shock, Clostridium difficile colitis, meningitis.

Musculoskeletal and Connective Tissue Disorders: Myositis, osteonecrosis, rhabdomyolysis, blood creatine kinase increased.

Neoplasms Benign, Malignant, and Unspecified (Including Cysts and Polyps): Abdominal neoplasm, anal cancer, basal cell carcinoma, Bowen’s disease, cholangiocarcinoma, diffuse large B-cell lymphoma, lymphoma, metastases to liver, esophageal carcinoma, nasopharyngeal carcinoma, squamous cell carcinoma, squamous cell carcinoma of skin, tongue neoplasm (malignant stage unspecified), anaplastic large cell lymphomas T- and null-cell types, bile duct neoplasms malignant, endocrine neoplasms malignant and unspecified.

Nervous System Disorders: Cerebrovascular accident, convulsions and epilepsy, tremor (excluding congenital), facial palsy, hemianopia, loss of consciousness, visual field defect.

Clinical Trials Experience in Pediatric Subjects

HIV-1–Infected Pediatric Subjects: Trial A4001031 is an open-label trial in which 103 treatment-experienced, CCR5-tropic, HIV-1–infected pediatric subjects aged 2 to less than 18 years weighing at least 10 kg received SELZENTRY twice daily in combination with OBT. The dose of SELZENTRY was based on body surface area (BSA) and on whether the subject was receiving potent CYP3A inhibitors and/or inducers. The median duration of therapy with SELZENTRY was 131 weeks with 72% of subjects receiving study treatment for greater than 48 weeks and 62% of subjects receiving study treatment for 96 weeks.

In these 103 children and adolescents, the safety profile through 96 weeks was similar to that for adults. Most of the adverse reactions reported were mild to moderate; severe (Grade 3 and 4) adverse reactions occurred in 2% of subjects. The most common adverse reactions (all grades) reported with twice-daily therapy with SELZENTRY were vomiting (12%), abdominal pain (4%), diarrhea (4%), nausea (4%), and dizziness (3%). Three subjects (3%) discontinued due to adverse events.

Maraviroc-related gastrointestinal adverse events through 48 weeks (nausea, vomiting, diarrhea, constipation, and abdominal pain/cramps) were observed more commonly in subjects who received the SELZENTRY oral solution (21%) compared with those who received SELZENTRY tablets (16%). Subjects were permitted to change formulations after Week 48.

HIV-1–Exposed Neonates: The IMPAACT P2007 trial was an open-label trial in which 47 full-term HIV-1–exposed neonates (born to HIV-1–infected mothers) received at least one dose of SELZENTRY in combination with other antiretrovirals, mostly zidovudine and/or nevirapine [see Clinical Pharmacology (12.3)]. Cohort 1 received 2 single doses of SELZENTRY: the first within 3 days of birth and the second at 7 to 14 days of age. Cohort 2 received SELZENTRY twice daily for 6 weeks beginning within 3 days of birth and continued through Week 6. Both cohorts received SELZENTRY with or without exposure to maternal efavirenz (in utero only in Cohort 1, and both in utero and after birth while breastfeeding in Cohort 2). The population was 51% male and 81% black. All infants were followed for safety through 16 weeks, with a total of 37 infants evaluable for safety.

There were no additional adverse reactions observed in neonates compared with those seen in adults. All adverse reactions reported were mild to moderate. The most common adverse reaction (all grades) reported with SELZENTRY was hemoglobin decreased (14%). One subject (3%) discontinued due to an adverse event (Grade 3 staphylococcal sepsis).

6.2 Postmarketing Experience

The following adverse events have been identified during postapproval use of SELZENTRY. Because these reactions are reported voluntarily from a population of uncertain size, it is not always possible to reliably estimate their frequency or establish a causal relationship to drug exposure.

Skin and Subcutaneous Tissue Disorders

Stevens‑Johnson syndrome (SJS), drug rash with eosinophilia and systemic symptoms (DRESS), toxic epidermal necrolysis (TEN).

7 DRUG INTERACTIONS

7.1 Effect of Concomitant Drugs on the Pharmacokinetics of Maraviroc

Maraviroc is metabolized by CYP3A and is also a substrate for P-glycoprotein (P-gp), organic anion-transporting polypeptide (OATP)1B1, and multidrug resistance-associated protein (MRP)2. The pharmacokinetics of maraviroc are likely to be modulated by inhibitors and inducers of CYP3A and P-gp and may be modulated by inhibitors of OATP1B1 and MRP2. Therefore, a dosage adjustment may be required when maraviroc is coadministered with those drugs [see Dosage and Administration (2.3, 2.4)].

Concomitant use of maraviroc and St. John's wort (Hypericum perforatum) or products containing St. John's wort is not recommended. Coadministration of maraviroc with St. John's wort is expected to substantially decrease maraviroc concentrations and may result in suboptimal levels of maraviroc and lead to loss of virologic response and possible resistance to maraviroc.

Additional drug interaction information is available [see Clinical Pharmacology (12.3)].

8 USE IN SPECIFIC POPULATIONS

8.1 Pregnancy

Pregnancy Exposure Registry

There is a pregnancy exposure registry that monitors pregnancy outcomes in women exposed to SELZENTRY during pregnancy. Physicians are encouraged to register patients by calling the Antiretroviral Pregnancy Registry (APR) at 1-800-258-4263.

Risk Summary

Limited data on the use of SELZENTRY during pregnancy from the APR and case reports are not sufficient to inform a drug-associated risk of birth defects and miscarriage. In animal reproduction studies, no evidence of adverse developmental outcomes was observed with maraviroc. During organogenesis in the rat and rabbit, systemic exposures (AUC) to maraviroc were approximately 20 times (rats) and 5 times (rabbits) the exposure in humans at the recommended 300-mg twice-daily dose. In the rat pre- and post-natal development study, maternal systemic exposure (AUC) to maraviroc was approximately 14 times the exposure in humans at the recommended 300-mg twice-daily dose (see Data).

The estimated background risk of major birth defects and miscarriage for the indicated population is unknown. All pregnancies have a background risk of birth defect, loss, or other adverse outcomes. In the U.S. general population, the estimated background risk of major birth defects and miscarriage in clinically recognized pregnancies is 2% to 4% and 15% to 20%, respectively.

Data

Animal Data: Maraviroc was administered orally to pregnant rats (up to 1,000 mg per kg per day) and rabbits (up to 75 mg per kg per day) on gestation Days 6 to 17 and 7 to 19, respectively. No adverse effects on embryo-fetal development were observed at these dose levels, resulting in exposures (AUC) approximately 20 times (rats) and 5 times (rabbits) higher than human exposures at the recommended daily dose. In the rat pre- and post-natal development study, maraviroc was administered orally at up to 1,000 mg per kg per day on gestation Day 6 to lactation/post-partum Day 20, with development of the offspring (including fertility and reproductive performance) unaffected by maternal administration of maraviroc at an exposure (AUC) approximately 14 times higher than human exposure at the recommended daily dose.

8.2 Lactation

Risk Summary

The Centers for Disease Control and Prevention recommend that HIV‑1–infected mothers in the United States not breastfeed their infants to avoid risking postnatal transmission of HIV‑1 infection.

There are no data on the presence of maraviroc in human milk, the effects on the breastfed infant, or the effects on milk production. When administered to lactating rats, maraviroc was present in milk (see Data). Because of the potential for (1) HIV transmission (in HIV-negative infants), (2) developing viral resistance (in HIV-positive infants), and (3) serious adverse reactions in a breastfed infant similar to those seen in adults, instruct mothers not to breastfeed if they are receiving SELZENTRY.

Data

Maraviroc (and related metabolites) was excreted into the milk of lactating rats following a single oral dose of maraviroc (100 mg per kg) on lactation Day 12, with a maximal milk concentration achieved one hour post-administration at a milk concentration approximately 2.5 times that of maternal plasma concentrations.

8.4 Pediatric Use

The safety and efficacy of SELZENTRY have been established in pediatric patients aged from birth to less than 18 years. The use of SELZENTRY in pediatric patients was supported by pharmacokinetic and safety data described below and by previous demonstration of efficacy in adult patients [see Indications and Usage (1), Dosage and Administration (2.4)].

HIV-1–Infected Pediatric Patients Aged 2 to Less Than 18 Years: The safety, pharmacokinetic profile, and antiviral activity of SELZENTRY were evaluated in treatment-experienced, CCR5-tropic, HIV-1–infected pediatric subjects aged 2 to less than 18 years weighing at least 10 kg in an open-label, multicenter clinical trial, A4001031 [see Adverse Reactions (6.1), Clinical Studies (14.2)]. Pharmacokinetics were evaluated in a total of 98 pediatric subjects: 85 subjects received SELZENTRY and concomitant medications that included potent CYP3A inhibitors with or without potent CYP3A inducers, 10 subjects received SELZENTRY and noninteracting medications (not containing potent CYP3A inhibitors or potent CYP3A inducers), and three subjects received SELZENTRY and medications that included potent CYP3A inducers without potent CYP3A inhibitors [see Clinical Pharmacology (12.3)].

HIV-1–Infected Pediatric Patients Aged Older Than 6 Weeks to Less Than 2 Years: No clinical trials have been conducted in children aged older than 6 weeks to less than 2 years. Dosing recommendations for SELZENTRY in this population when concomitantly receiving noninteracting medications are based on population pharmacokinetic modeling and simulation only [see Dosage and Administration (2.4), Clinical Pharmacology (12.3)].

HIV-1–Infected Neonates Aged from Birth to 6 Weeks: The recommendation of SELZENTRY for the treatment of HIV-1 infection in this pediatric population is based on safety and pharmacokinetic data obtained from clinical trial IMPAACT P2007. In IMPAACT P2007, the safety and pharmacokinetic profiles of SELZENTRY were evaluated in full-term HIV-1–exposed neonates (born to HIV-1–infected mothers) aged from birth through 6 weeks [see Adverse Reactions (6.1)]. Pharmacokinetics were evaluated in 38 of 47 enrolled neonates who received SELZENTRY as a single dose (n = 13) or multiple doses (n = 25) up to 6 weeks of age concomitantly with other antiretrovirals (mostly zidovudine and/or nevirapine) with or without maternal exposure to efavirenz. HIV-1 status was assessed by nucleic acid test at birth, Week 6, and Week 16; all 47 enrolled neonates were HIV-1 negative at completion of the study [see Clinical Pharmacology (12.3)].

There are insufficient data to make dosing recommendations for use of SELZENTRY in pediatric patients concomitantly receiving potent CYP3A inhibitors and weighing less than 10 kg, or in any pediatric patients concomitantly receiving potent CYP3A inducers without a potent CYP3A inhibitor [see Dosage and Administration (2.4, 2.5)].

SELZENTRY is not recommended in pre-term neonates or in pediatric patients weighing less than 2 kg.

8.5 Geriatric Use

There were insufficient numbers of subjects aged 65 and over in the clinical trials to determine whether they respond differently from younger subjects. In general, caution should be exercised when administering SELZENTRY in elderly patients, also reflecting the greater frequency of decreased hepatic and renal function, of concomitant disease and other drug therapies.

8.6 Renal Impairment

Recommended doses of SELZENTRY for adult patients with impaired renal function (CrCl less than or equal to 80 mL per minute) are based on the results of a pharmacokinetic trial conducted in healthy adult subjects with various degrees of renal impairment. Maraviroc has not been studied in pediatric patients with renal impairment. There are no data to recommend specific doses of SELZENTRY in pediatric patients with mild to moderate renal impairment [see Use in Specific Populations (8.4)]. SELZENTRY is contraindicated in pediatric patients with severe renal impairment or ESRD on regular hemodialysis who are receiving potent CYP3A inhibitors [see Contraindications (4)].

The pharmacokinetics of maraviroc in adult subjects with mild and moderate renal impairment was similar to that in subjects with normal renal function [see Clinical Pharmacology (12.3)]. A limited number of adult subjects with mild and moderate renal impairment in the Phase 3 clinical trials (n = 131 and n = 12, respectively) received the same dose of SELZENTRY as that administered to subjects with normal renal function. In these subjects, there was no apparent difference in the adverse event profile for maraviroc compared with subjects with normal renal function.

If adult patients with severe renal impairment or ESRD not receiving a concomitant potent CYP3A inhibitor or inducer experience any symptoms of postural hypotension while taking SELZENTRY 300 mg twice daily, the dose should be reduced to 150 mg twice daily. No trials have been performed in subjects with severe renal impairment or ESRD co-treated with potent CYP3A inhibitors or inducers. Hence, no dose of SELZENTRY can be recommended, and SELZENTRY is contraindicated for these patients [see Dosage and Administration (2.3), Contraindications (4), Warnings and Precautions (5.3), Clinical Pharmacology (12.3)].

8.7 Hepatic Impairment

Maraviroc is principally metabolized by the liver; therefore, when administering this drug to patients with hepatic impairment, maraviroc concentrations may be increased. Maraviroc concentrations are higher when SELZENTRY 150 mg is administered with a potent CYP3A inhibitor compared with following administration of 300 mg without a CYP3A inhibitor, so patients with moderate hepatic impairment who receive SELZENTRY 150 mg with a potent CYP3A inhibitor should be monitored closely for maraviroc-associated adverse events. Maraviroc has not been studied in subjects with severe hepatic impairment or in pediatric patients with any degree of hepatic impairment [see Warnings and Precautions (5.1), Clinical Pharmacology (12.3)].

10 OVERDOSAGE

The highest single dose administered in clinical trials was 1,200 mg. The dose-limiting adverse event was postural hypotension, which was observed at 600 mg. While the recommended dose for SELZENTRY in patients receiving a CYP3A inducer without a CYP3A inhibitor is 600 mg twice daily, this dose is appropriate due to enhanced metabolism.

Prolongation of the QT interval was seen in dogs and monkeys at plasma concentrations 6 and 12 times, respectively, those expected in humans at the intended exposure of 300-mg equivalents twice daily. However, no significant QT prolongation was seen in the trials in treatment-experienced subjects with HIV using the recommended doses of maraviroc, or in a specific pharmacokinetic trial to evaluate the potential of maraviroc to prolong the QT interval [see Clinical Pharmacology (12.2)].

There is no specific antidote for overdose with maraviroc. Treatment of overdose should consist of general supportive measures including keeping the patient in a supine position, careful assessment of patient vital signs, blood pressure, and electrocardiogram.

Administration of activated charcoal may also be used to aid in removal of unabsorbed drug. Hemodialysis had a minimal effect on maraviroc clearance and exposure in a trial in subjects with ESRD [see Clinical Pharmacology (12.3)].

11 DESCRIPTION

SELZENTRY (maraviroc) is a selective, slowly reversible, small molecule antagonist of the interaction between human CCR5 and HIV-1 gp120. Blocking this interaction prevents CCR5-tropic HIV-1 entry into cells.

SELZENTRY film-coated tablets for oral administration contain 25, 75, 150, or 300 mg of maraviroc and the following inactive ingredients: dibasic calcium phosphate (anhydrous), magnesium stearate, microcrystalline cellulose, and sodium starch glycolate. The film coat (Opadry II Blue [85G20583]) contains FD&C blue #2 aluminum lake, soya lecithin, polyethylene glycol (macrogol 3350), polyvinyl alcohol, talc, and titanium dioxide.

SELZENTRY oral solution contains 20 mg per mL of maraviroc and the following inactive ingredients: citric acid (anhydrous), purified water, sodium benzoate, sodium citrate dihydrate, strawberry flavoring (501440T), and sucralose.

Maraviroc is chemically described as 4,4-difluoro-N-{(1S)-3-[exo-3-(3-isopropyl-5-methyl-4H-1,2,4-triazol-4-yl)-8-azabicyclo[3.2.1]oct-8-yl]-1-phenylpropyl}cyclohexanecarboxamide.

The molecular formula is C29H41F2N5O and the structural formula is:

Maraviroc is a white to pale-colored powder with a molecular weight of 513.67. It is highly soluble across the physiological pH range (pH 1.0 to 7.5).

12 CLINICAL PHARMACOLOGY

12.1 Mechanism of Action

Maraviroc is an HIV-1 antiviral drug [see Microbiology (12.4)].

12.2 Pharmacodynamics

Exposure-Response Relationship in Treatment-Experienced Adult Subjects

The relationship between maraviroc, modeled plasma trough concentration (Cmin) (1 to 9 samples per subject taken on up to 7 visits), and virologic response was evaluated in 973 treatment-experienced HIV-1-infected subjects with varied optimized background antiretroviral regimens in Trials A4001027 and A4001028. The Cmin, baseline viral load, baseline CD4^+ cell count, and overall sensitivity score (OSS) were found to be important predictors of virologic success (defined as viral load less than 400 copies per mL at 24 weeks). Table 9 illustrates the proportions of subjects with virologic success (%) within each Cmin quartile for 150-mg twice-daily and 300-mg twice-daily groups.

Table 9. Treatment-Experienced Subjects with Virologic Success by Cmin Quartile (Q1-Q4)
 | 150 mg Twice Daily (with CYP3A Inhibitors) |  |  | 300 mg Twice Daily (without CYP3A Inhibitors)
 | n | Median Cmin | % Subjects with Virologic Success | n | Median Cmin | % Subjects with Virologic Success
Placebo | 160 | - | 30.6 | 35 | - | 28.6
Q1 | 78 | 33 | 52.6 | 22 | 13 | 50.0
Q2 | 77 | 87 | 63.6 | 22 | 29 | 68.2
Q3 | 78 | 166 | 78.2 | 22 | 46 | 63.6
Q4 | 78 | 279 | 74.4 | 22 | 97 | 68.2

Exposure-Response Relationship in Treatment-Naive Adult Subjects

The relationship between maraviroc, modeled plasma trough concentration (Cmin) (1 to 12 samples per subject taken on up to 8 visits), and virologic response was evaluated in 294 treatment-naive HIV–1-infected subjects receiving maraviroc 300 mg twice daily in combination with lamivudine/zidovudine in Trial A4001026. Table 10 illustrates the proportion (%) of subjects with virologic success less than 50 copies per mL at 48 weeks within each Cmin quartile for the 300-mg twice-daily dose.

Table 10. Treatment-Naive Subjects with Virologic Success by Cmin Quartile (Q1-Q4)
 | 300 mg Twice Daily
 | n | Median Cmin | % Subjects with Virologic Success
Q1 | 75 | 23 | 57.3
Q2 | 72 | 39 | 72.2
Q3 | 73 | 56 | 74.0
Q4 | 74 | 81 | 83.8

Eighteen of 75 (24%) subjects in Q1 had no measurable maraviroc concentration on at least one occasion versus 1 of 73 and 1 of 74 in Q3 and Q4, respectively.

Effects on Electrocardiogram

A placebo-controlled, randomized, crossover trial to evaluate the effect on the QT interval of healthy male and female volunteers was conducted with 3 single oral doses of maraviroc and moxifloxacin. The placebo-adjusted mean maximum (upper 1-sided 95% CI) increases in QTc from baseline after 100, 300, and 900 mg of maraviroc were –2 (0), -1 (1), and 1 (3) msec, respectively, and 13 (15) msec for moxifloxacin 400 mg. No subject in any group had an increase in QTc of greater than or equal to 60 msec from baseline. No subject experienced an interval exceeding the potentially clinically relevant threshold of 500 msec.

12.3 Pharmacokinetics

Table 11. Mean Maraviroc Pharmacokinetic Parameters in Adults
Patient Population | Maraviroc Dose | n | AUC12 (ng.h/mL) | Cmax (ng/mL) | Cmin (ng/mL)
Healthy volunteers (Phase 1) | 300 mg twice daily | 64 | 2,908 | 888 | 43.1
Asymptomatic HIV subjects (Phase 2a) | 300 mg twice daily | 8 | 2,550 | 618 | 33.6
Treatment-experienced HIV subjects (Phase 3)a | 300 mg twice daily | 94 | 1,513 | 266 | 37.2
Treatment-experienced HIV subjects (Phase 3)a | 150 mg twice daily; (+ CYP3A inhibitor) | 375 | 2,463 | 332 | 101
Treatment-naive HIV subjects (Phase 2b/3)a | 300 mg twice daily | 344 | 1,865 | 287 | 60
a The estimated exposure is lower compared with other trials possibly due to sparse sampling, food effect, compliance, and concomitant medications.

Absorption

Peak maraviroc plasma concentrations are attained 0.5 to 4 hours following single oral doses of 1 to 1,200 mg administered to uninfected volunteers. The pharmacokinetics of oral maraviroc are not dose proportional over the dose range.

The absolute bioavailability of a 100‑mg dose is 23% and is predicted to be 33% at 300 mg. Maraviroc is a substrate for the efflux transporter P-gp.

Effect of Food on Oral Absorption: Coadministration of a 300‑mg tablet with a high‑fat breakfast reduced maraviroc Cmax and AUC by 33% and coadministration of 75 mg of oral solution with a high-fat breakfast reduced maraviroc AUC by 73% in healthy adult volunteers. Studies with the tablet formulation demonstrated a reduced food effect at higher doses.

There were no food restrictions in the adult trials (using the tablet formulation) or in the pediatric trial (using both tablet and oral solution formulations) that demonstrated the efficacy/antiviral activity and safety of maraviroc [see Clinical Studies (14.1, 14.2)].

Distribution

Maraviroc is bound (approximately 76%) to human plasma proteins, and shows moderate affinity for albumin and alpha‑1 acid glycoprotein. The volume of distribution of maraviroc is approximately 194 L.

Elimination

Metabolism: Trials in humans and in vitro studies using human liver microsomes and expressed enzymes have demonstrated that maraviroc is principally metabolized by the cytochrome P450 system to metabolites that are essentially inactive against HIV‑1. In vitro studies indicate that CYP3A is the major enzyme responsible for maraviroc metabolism. In vitro studies also indicate that polymorphic enzymes CYP2C9, CYP2D6, and CYP2C19 do not contribute significantly to the metabolism of maraviroc.

Maraviroc is the major circulating component (~42% drug‑related radioactivity) following a single oral dose of 300 mg [^14C]-maraviroc. The most significant circulating metabolite in humans is a secondary amine (~22% radioactivity) formed by N‑dealkylation. This polar metabolite has no significant pharmacological activity. Other metabolites are products of mono‑oxidation and are only minor components of plasma drug‑related radioactivity.

Excretion: The terminal half‑life of maraviroc following oral dosing to steady state in healthy subjects was 14 to 18 hours. A mass balance/excretion trial was conducted using a single 300‑mg dose of ^14C-labeled maraviroc. Approximately 20% of the radiolabel was recovered in the urine and 76% was recovered in the feces over 168 hours. Maraviroc was the major component present in urine (mean of 8% dose) and feces (mean of 25% dose). The remainder was excreted as metabolites.

Specific Populations

Patients with Hepatic Impairment: Maraviroc is primarily metabolized and eliminated by the liver. A trial compared the pharmacokinetics of a single 300‑mg dose of SELZENTRY in subjects with mild (Child‑Pugh Class A, n = 8) and moderate (Child‑Pugh Class B, n = 8) hepatic impairment with pharmacokinetics in healthy subjects (n = 8). The mean Cmax and AUC were 11% and 25% higher, respectively, for subjects with mild hepatic impairment, and 32% and 46% higher, respectively, for subjects with moderate hepatic impairment compared with subjects with normal hepatic function. These changes do not warrant a dose adjustment. Maraviroc concentrations are higher when SELZENTRY 150 mg is administered with a potent CYP3A inhibitor compared with following administration of 300 mg without a CYP3A inhibitor, so patients with moderate hepatic impairment who receive SELZENTRY 150 mg with a potent CYP3A inhibitor should be monitored closely for maraviroc‑associated adverse events. The pharmacokinetics of maraviroc have not been studied in subjects with severe hepatic impairment [see Warnings and Precautions (5.1)].

Patients with Renal Impairment: A trial compared the pharmacokinetics of a single 300‑mg dose of SELZENTRY in adult subjects with severe renal impairment (CrCl less than 30 mL per minute, n = 6) and ESRD (n = 6) with healthy volunteers (n = 6). Geometric mean ratios for maraviroc Cmax and AUCinf were 2.4‑fold and 3.2‑fold higher, respectively, for subjects with severe renal impairment, and 1.7‑fold and 2.0‑fold higher, respectively, for subjects with ESRD as compared with subjects with normal renal function in this trial. Hemodialysis had a minimal effect on maraviroc clearance and exposure in subjects with ESRD. Exposures observed in subjects with severe renal impairment and ESRD were within the range observed in previous 300‑mg single‑dose trials of SELZENTRY in healthy volunteers with normal renal function. However, maraviroc exposures in the subjects with normal renal function in this trial were 50% lower than those observed in previous trials. Based on the results of this trial, no dose adjustment is recommended for patients with renal impairment receiving SELZENTRY without a potent CYP3A inhibitor or inducer. However, if patients with severe renal impairment or ESRD experience any symptoms of postural hypotension while taking SELZENTRY 300 mg twice daily, their dose should be reduced to 150 mg twice daily [see Dosage and Administration (2.3), Warnings and Precautions (5.3)].

In addition, the trial compared the pharmacokinetics of multiple‑dose SELZENTRY in combination with saquinavir/ritonavir 1,000/100 mg twice daily (a potent CYP3A inhibitor combination) for 7 days in subjects with mild renal impairment (CrCl greater than 50 and less than or equal to 80 mL per minute, n = 6) and moderate renal impairment (CrCl greater than or equal to 30 and less than or equal to 50 mL per minute, n = 6) with healthy volunteers with normal renal function (n = 6). Subjects received 150 mg of SELZENTRY at different dose frequencies (healthy volunteers – every 12 hours; mild renal impairment – every 24 hours; moderate renal impairment – every 48 hours). Compared with healthy volunteers (dosed every 12 hours), geometric mean ratios for maraviroc AUCtau, Cmax, and Cmin were 50% higher, 20% higher, and 43% lower, respectively, for subjects with mild renal impairment (dosed every 24 hours). Geometric mean ratios for maraviroc AUCtau, Cmax, and Cmin were 16% higher, 29% lower, and 85% lower, respectively, for subjects with moderate renal impairment (dosed every 48 hours) compared with healthy volunteers (dosed every 12 hours). Based on the data from this trial, no adjustment in dose is recommended for patients with mild or moderate renal impairment [see Dosage and Administration (2.3)].

Pediatric Patients: Aged 2 to Less Than 18 Years: The pharmacokinetics of maraviroc were evaluated in CCR5-tropic, HIV-1–infected, treatment-experienced pediatric subjects aged 2 to less than 18 years. In the dose-finding stage of Trial A4001031, doses were administered with food on intensive pharmacokinetic evaluation days and optimized to achieve an average concentration over the dosing interval (Cavg) of greater than 100 ng per mL. Throughout the trial, on non-intensive pharmacokinetic evaluation days maraviroc was taken with or without food. The initial dose of maraviroc was based on BSA and concomitant medication category (i.e., presence of CYP3A inhibitors and/or inducers). The conversion of dosing to a weight (kg)-band basis in children provides comparable exposures with those observed in the trial at the corresponding BSA.

Maraviroc pharmacokinetic parameters in pediatric subjects aged 2 to less than 18 years receiving potent CYP3A inhibitors with or without a potent CYP3A inducer were similar to those observed in adults (Table 12).

Table 12. Maraviroc Pharmacokinetic Parameters in Treatment-Experienced Pediatric Patients Receiving SELZENTRY with Potent CYP3A Inhibitors (with or without a Potent CYP3A Inducer)
Weight | Dose of SELZENTRY | Maraviroc Pharmacokinetic Parametera; Geometric Mean
Weight | Dose of SELZENTRY | AUC12 (ng.h/mL) | Cavg (ng/mL) | Cmax (ng/mL) | Cmin (ng/mL)
10 kg to <20 kg | 50 mg twice daily | 2,349 | 196 | 324 | 78
20 kg to <30 kg | 75 mg twice daily | 3,020 | 252 | 394 | 118
30 kg to <40 kg | 100 mg twice daily | 3,229 | 269 | 430 | 126
≥40 kg | 150 mg twice daily | 4,044 | 337 | 563 | 152
a Model-predicted steady-state pharmacokinetic parameters are presented.

Aged from Birth to Less Than 6 Weeks: The pharmacokinetics of maraviroc were evaluated in 38 of 47 enrolled HIV-1–exposed neonates (born to HIV-1–infected mothers) aged from birth up to 6 weeks [see Adverse Reactions (6.1)]. In the IMPAACT P2007 trial, 13 neonates received weight-based maraviroc dosing as single doses at birth and approximately 7 days, and 25 neonates received maraviroc twice daily up to 6 weeks of age without exposure to potent CYP3A inhibitors and/or inducers. Maraviroc pharmacokinetic parameters in neonates weighing at least 2 kg at birth (Table 13) were similar to those observed in adults. Exposure to maternal efavirenz both in utero (for a minimum of 2 weeks immediately prior to delivery) and after birth while breastfeeding did not have a meaningful impact on maraviroc pharmacokinetic parameters.

Table 13. Maraviroc Pharmacokinetic Parameters in Full-Term Neonates (Birth Up to 6 Weeks of Age) Receiving SELZENTRY with Noninteracting Concomitant Medicationsa
Pharmacokinetic Sampling Time | n | Median Dose (range) | Maraviroc Pharmacokinetic Parameter; Geometric Mean
Pharmacokinetic Sampling Time | n | Median Dose (range) | AUC12 (ng.h/mL) | Cavg (ng/mL) | Cmax (ng/mL) | Cmin (ng/mL)
Day 1 | 13 | 30 mg (20 to 40 mg) single dose | 3,510b | 292 | 380 | -
Week 1 | 25 | 25 mg (20 to 30 mg); twice daily | 1,216 | 101 | 262 | 23
Week 4 | 25 | 30 mg (20 to 40 mg); twice daily | 1,385 | 115 | 295 | 43
a Noninteracting concomitant medications include all medications that are not potent CYP3A inhibitors or inducers.
b AUCinf calculated for single-dose pharmacokinetics.

Clinical pharmacokinetic data with maraviroc in pediatric patients aged older than 6 weeks to less than 2 years are not available and clinical pharmacokinetic data in pediatric patients aged 2 to less than 18 years receiving noninteracting concomitant medications are limited. Based on population pharmacokinetic modeling and simulation, the recommended dosing regimen of SELZENTRY for this population is predicted to result in similar maraviroc exposures when compared with exposures achieved in adults receiving SELZENTRY 300 mg twice daily (with noninteracting concomitant medications) [see Dosage and Administration (2.4)].

Geriatric Patients: Pharmacokinetics of maraviroc have not been fully evaluated in the elderly (aged 65 years and older). Based on population pharmacokinetic analyses, age did not have a clinically relevant effect on maraviroc exposure in subjects up to age 65 years [see Use in Specific Populations (8.5)].

Race and Gender: Based on population pharmacokinetics and 2 clinical CYP3A5 genotype analyses for race, no dosage adjustment is recommended based on race or gender.

Drug Interaction Studies

Effect of Concomitant Drugs on the Pharmacokinetics of Maraviroc: Maraviroc is a substrate of CYP3A and P-gp and hence its pharmacokinetics are likely to be modulated by inhibitors and inducers of these enzymes/transporters. The CYP3A/P-gp inhibitors ketoconazole, lopinavir/ritonavir, ritonavir, darunavir/ritonavir, saquinavir/ritonavir, and atazanavir ± ritonavir all increased the Cmax and AUC of maraviroc (Table 14). The CYP3A and/or P-gp inducers rifampin, etravirine, and efavirenz decreased the Cmax and AUC of maraviroc (Table 14). While not studied, potent CYP3A and/or P-gp inducers carbamazepine, phenobarbital, and phenytoin are expected to decrease maraviroc concentrations. Based on in vitro study results, maraviroc is also a substrate of OATP1B1 and MRP2; its pharmacokinetics may be modulated by inhibitors of these transporters.

Tipranavir/ritonavir (net CYP3A inhibitor/P-gp inducer) did not affect the steady‑state pharmacokinetics of maraviroc (Table 14). Cotrimoxazole and tenofovir did not affect the pharmacokinetics of maraviroc.

Table 14. Effect of Coadministered Agents on the Pharmacokinetics of Maraviroc
Coadministered Drug; and Dose | n | Dose of SELZENTRY | Ratio (90% CI) of Maraviroc Pharmacokinetic Parameters with/without Coadministered Drug; (No Effect = 1.00)
Coadministered Drug; and Dose | n | Dose of SELZENTRY | Cmin | AUCtau | Cmax
CYP3A and/or P-gp Inhibitors
Ketoconazole; 400 mg q.d. | 12 | 100 mg b.i.d. | 3.75; (3.01, 4.69) | 5.00; (3.98, 6.29) | 3.38; (2.38, 4.78)
Ritonavir; 100 mg b.i.d. | 8 | 100 mg b.i.d. | 4.55; (3.37, 6.13) | 2.61; (1.92, 3.56) | 1.28; (0.79, 2.09)
Saquinavir (soft gel capsules) /ritonavir; 1,000 mg/100 mg b.i.d. | 11 | 100 mg b.i.d. | 11.3; (8.96, 14.1) | 9.77; (7.87, 12.14) | 4.78; (3.41, 6.71)
Lopinavir/ritonavir; 400 mg/100 mg b.i.d. | 11 | 300 mg b.i.d. | 9.24; (7.98, 10.7) | 3.95; (3.43, 4.56) | 1.97; (1.66, 2.34)
Atazanavir; 400 mg q.d. | 12 | 300 mg b.i.d. | 4.19; (3.65, 4.80) | 3.57; (3.30, 3.87) | 2.09; (1.72, 2.55)
Atazanavir/ritonavir; 300 mg/100 mg q.d. | 12 | 300 mg b.i.d. | 6.67; (5.78, 7.70) | 4.88; (4.40, 5.41) | 2.67; (2.32, 3.08)
Darunavir/ritonavir; 600 mg/100 mg b.i.d. | 12 | 150 mg b.i.d. | 8.00; (6.35, 10.1) | 4.05; (2.94, 5.59) | 2.29; (1.46, 3.59)
Elvitegravir/ritonavir; 150 mg/100 mg q.d. | 11 | 150 mg b.i.d. | 4.23; (3.47, 5.16) | 2.86; (2.33, 3.51) | 2.15; (1.71, 2.69)
CYP3A and/or P-gp Inducers
Efavirenz; 600 mg q.d. | 12 | 100 mg b.i.d. | 0.55; (0.43, 0.72) | 0.55; (0.49, 0.62) | 0.49; (0.38, 0.63)
Efavirenz; 600 mg q.d. | 12 | 200 mg b.i.d.; (+ efavirenz):; 100 mg b.i.d. (alone) | 1.09; (0.89, 1.35) | 1.15; (0.98, 1.35) | 1.16; (0.87, 1.55)
Rifampicin; 600 mg q.d. | 12 | 100 mg b.i.d. | 0.22; (0.17, 0.28) | 0.37; (0.33, 0.41) | 0.34; (0.26, 0.43)
Rifampicin; 600 mg q.d. | 12 | 200 mg b.i.d.; (+ rifampicin):; 100 mg b.i.d. (alone) | 0.66; (0.54, 0.82) | 1.04; (0.89, 1.22) | 0.97; (0.72, 1.29)
Etravirine; 200 mg b.i.d. | 14 | 300 mg b.i.d. | 0.61; (0.53, 0.71) | 0.47; (0.38, 0.58) | 0.40; (0.28, 0.57)
Nevirapinea; 200 mg b.i.d. (+ lamivudine 150 mg b.i.d., tenofovir 300 mg q.d.) | 8 | 300 mg; single dose | – | 1.01; (0.65, 1.55) | 1.54; (0.94, 2.51)
CYP3A and/or P-gp Inhibitors and Inducers
Lopinavir/ritonavir + efavirenz; 400 mg/100 mg b.i.d. + 600 mg q.d. | 11 | 300 mg b.i.d. | 6.29; (4.72, 8.39) | 2.53; (2.24, 2.87) | 1.25; (1.01, 1.55)
Saquinavir (soft gel capsules) /ritonavir + efavirenz 1,000 mg/100 mg b.i.d. + 600 mg q.d. | 11 | 100 mg b.i.d. | 8.42; (6.46, 10.97) | 5.00; (4.26, 5.87) | 2.26; (1.64, 3.11)
Darunavir/ritonavir + etravirine; 600 mg/100 mg b.i.d. + 200 mg b.i.d. | 10 | 150 mg b.i.d. | 5.27; (4.51, 6.15) | 3.10; (2.57, 3.74) | 1.77; (1.20, 2.60)
Fosamprenavir/ritonavir; 700 mg/100 mg b.i.d. | 14 | 300 mg b.i.d. | 4.74; (4.03, 5.57) | 2.49; (2.19, 2.82) | 1.52; (1.27, 1.82)
Fosamprenavir/ritonavir; 1,400 mg/100 mg q.d. | 14 | 300 mg q.d. | 1.80; (1.53, 2.13) | 2.26; (1.99, 2.58) | 1.45; (1.20, 1.74)
Tipranavir/ritonavir; 500 mg/200 mg b.i.d. | 12 | 150 mg b.i.d. | 1.80; (1.55, 2.09) | 1.02; (0.85, 1.23) | 0.86; (0.61, 1.21)
Other
Raltegravir; 400 mg b.i.d. | 17 | 300 mg b.i.d. | 0.90; (0.85, 0.96) | 0.86; (0.80, 0.92) | 0.79; (0.67, 0.94)
a Compared with historical data.

Effect of Maraviroc on the Pharmacokinetics of Concomitant Drugs: Maraviroc is unlikely to inhibit the metabolism of coadministered drugs metabolized by the following cytochrome P enzymes (CYP1A2, CYP2B6, CYP2C8, CYP2C9, CYP2C19, and CYP3A) or to inhibit the uptake of OATP1B1 or the export of MRP2 because maraviroc did not inhibit activity of those enzymes or transporters at clinically relevant concentrations in vitro. Maraviroc does not induce CYP1A2 in vitro. Additionally, in vitro studies have shown that maraviroc is not a substrate for, and does not inhibit, any of the major renal uptake inhibitors (organic anion transporter [OAT]1, OAT3, organic cation transporter [OCT]2, novel organic cation transporter [OCTN]1, and OCTN2) at clinically relevant concentrations.

In vitro results suggest that maraviroc could inhibit P-gp in the gut. However, maraviroc did not significantly affect the pharmacokinetics of digoxin in vivo, indicating maraviroc may not significantly inhibit or induce P-gp clinically.

Drug interaction trials were performed with maraviroc and other drugs likely to be coadministered or commonly used as probes for pharmacokinetic interactions (Table 14).

Coadministration of fosamprenavir 700 mg/ritonavir 100 mg twice daily and maraviroc 300 mg twice daily decreased the Cmin and AUC of amprenavir by 36% and 35%, respectively. Coadministration of fosamprenavir 1,400 mg/ritonavir 100 mg once daily and maraviroc 300 mg once daily decreased the Cmin and AUC of amprenavir by 15% and 30%, respectively. No dosage adjustment is necessary when SELZENTRY is dosed 150 mg twice daily in combination with fosamprenavir/ritonavir dosed once or twice daily. Fosamprenavir should be given with ritonavir when coadministered with SELZENTRY.

Maraviroc had no significant effect on the pharmacokinetics of elvitegravir, zidovudine, or lamivudine. Maraviroc decreased the Cmin and AUC of raltegravir by 27% and 37%, respectively, which is not clinically significant. Maraviroc had no clinically relevant effect on the pharmacokinetics of midazolam, the oral contraceptives ethinylestradiol and levonorgestrel, no effect on the urinary 6β-hydroxycortisol/cortisol ratio, suggesting no induction of CYP3A in vivo. Maraviroc had no effect on the debrisoquine metabolic ratio (MR) at 300 mg twice daily or less in vivo and did not cause inhibition of CYP2D6 in vitro until concentrations greater than 100 microM. However, there was 234% increase in debrisoquine MR on treatment compared with baseline at 600 mg once daily, suggesting potential inhibition of CYP2D6 at higher doses.

12.4 Microbiology

Mechanism of Action

Maraviroc is a member of a therapeutic class called CCR5 co-receptor antagonists. Maraviroc selectively binds to the human chemokine receptor CCR5 present on the cell membrane, preventing the interaction of HIV-1 gp120 and CCR5 necessary for CCR5-tropic HIV-1 to enter cells. CXCR4-tropic and dual-tropic HIV-1 entry is not inhibited by maraviroc.

Antiviral Activity in Cell Culture

Maraviroc inhibits the replication of CCR5-tropic laboratory strains and primary isolates of HIV-1 in models of acute peripheral blood leukocyte infection. The mean EC50 value (50% effective concentration) for maraviroc against HIV-1 group M isolates (subtypes A to J and circulating recombinant form AE) and group O isolates ranged from 0.1 to 4.5 nM (0.05 to 2.3 ng per mL) in cell culture.

When used with other antiretroviral agents in cell culture, the combination of maraviroc was not antagonistic with non-nucleoside reverse transcriptase inhibitors (NNRTIs: efavirenz and nevirapine), NRTIs (abacavir, didanosine, emtricitabine, lamivudine, stavudine, tenofovir, zalcitabine, and zidovudine), or protease inhibitors (PIs: amprenavir, atazanavir, darunavir, indinavir, lopinavir, nelfinavir, ritonavir, saquinavir, and tipranavir). Maraviroc was not antagonistic with the HIV-1 gp41 fusion inhibitor enfuvirtide. Maraviroc was not active against CXCR4-tropic and dual-tropic viruses (EC50 value greater than 10 microM). The antiviral activity of maraviroc against HIV-2 has not been evaluated.

Resistance in Cell Culture: HIV-1 variants with reduced susceptibility to maraviroc have been selected in cell culture following serial passage of 2 CCR5-tropic viruses (CCl/85 and RU570). The maraviroc-resistant viruses remained CCR5-tropic with no evidence of a change from a CCR5-tropic virus to a CXCR4-using virus. Two amino acid residue substitutions in the V3-loop region of the HIV-1 envelope glycoprotein (gp160), A316T, and I323V (HXB2 numbering), were shown to be necessary for the maraviroc-resistant phenotype in the HIV-1 isolate CCl/85. In the RU570 isolate a 3-amino acid residue deletion in the V3 loop, ΔQAI (HXB2 positions 315 to 317), was associated with maraviroc resistance. The relevance of the specific gp120 substitutions observed in maraviroc-resistant isolates selected in cell culture to clinical maraviroc resistance is not known. Maraviroc-resistant viruses were characterized phenotypically by concentration-response curves that did not reach 100% inhibition in phenotypic drug assays, rather than increases in EC50 values.

Cross-Resistance in Cell Culture: Maraviroc had antiviral activity against HIV‑1 clinical isolates resistant to NNRTIs, NRTIs, PIs, and the gp41 fusion inhibitor enfuvirtide in cell culture (EC50 values ranged from 0.7 to 8.9 nM [0.36 to 4.57 ng per mL]). Maraviroc‑resistant viruses that emerged in cell culture remained susceptible to enfuvirtide and the protease inhibitor saquinavir.

Clinical Resistance: Virologic failure on maraviroc can result from genotypic and phenotypic resistance to maraviroc, through outgrowth of undetected CXCR4-using virus present before maraviroc treatment (see Tropism), through resistance to background therapy drugs (Table 15), or due to low exposure to maraviroc [see Clinical Pharmacology (12.2)].

Antiretroviral Treatment-Experienced Adult Subjects (Trials A4001027 and A4001028): Week 48 data from treatment-experienced subjects failing maraviroc-containing regimens with CCR5-tropic virus (n = 58) have identified 22 viruses that had decreased susceptibility to maraviroc characterized in phenotypic drug assays by concentration-response curves that did not reach 100% inhibition. Additionally, CCR5-tropic virus from 2 of these treatment-failure subjects had greater than or equal to 3-fold shifts in EC50 values for maraviroc at the time of failure.

Fifteen of these viruses were sequenced in the gp120 encoding region and multiple amino acid substitutions with unique patterns in the heterogeneous V3 loop region were detected. Changes at either amino acid position 308 or 323 (HXB2 numbering) were seen in the V3 loop in 7 of the subjects with decreased maraviroc susceptibility. Substitutions outside the V3 loop of gp120 may also contribute to reduced susceptibility to maraviroc.

Antiretroviral Treatment-Naive Adult Subjects (Trial A4001026): Treatment-naive subjects receiving SELZENTRY had more virologic failures and more treatment-emergent resistance to the background regimen drugs compared with those receiving efavirenz (Table 15).

Table 15. Development of Resistance to Maraviroc or Efavirenz and Background Drugs in Antiretroviral Treatment-Naive Trial A4001026 for Patients with Only CCR5-Tropic Virus at Screening Using Enhanced Sensitivity TROFILE Assay
 | Maraviroc | Efavirenz
Total N in dataset (as-treated) | 273 | 241
Total virologic failures (as-treated) | 85 (31%) | 56 (23%)
Evaluable virologic failures with post baseline genotypic and phenotypic data | 73 | 43
Lamivudine resistance | 39 (53%) | 13 (30%)
Zidovudine resistance | 2 (3%) | 0
Efavirenz resistance | – | 23 (53%)
Phenotypic resistance to maraviroca | 19 (26%) | –
a Includes subjects failing with CXCR4- or dual/mixed-tropism because these viruses are not intrinsically susceptible to maraviroc.

In an as‑treated analysis of treatment‑naive subjects at 96 weeks, 32 subjects failed a maraviroc‑containing regimen with CCR5‑tropic virus and had a tropism result at failure; 7 of these subjects had evidence of maraviroc phenotypic resistance defined as concentration‑response curves that did not reach 95% inhibition. One additional subject had a greater than or equal to 3‑fold shift in the EC50 value for maraviroc at the time of failure. A clonal analysis of the V3 loop amino acid envelope sequences was performed from 6 of the 7 subjects. Changes in V3 loop amino acid sequence differed between each of these different subjects, even for those infected with the same virus clade, suggesting that there are multiple diverse pathways to maraviroc resistance. The subjects who failed with CCR5‑tropic virus and without a detectable maraviroc shift in susceptibility were not evaluated for genotypic resistance.

Of the 32 maraviroc virologic failures failing with CCR5‑tropic virus, 20 (63%) also had genotypic and/or phenotypic resistance to background drugs in the regimen (lamivudine, zidovudine).

Tropism: In both treatment‑experienced and treatment‑naive subjects, detection of CXCR4‑using virus prior to initiation of therapy has been associated with a reduced virologic response to maraviroc.

Antiretroviral Treatment‑Experienced Subjects (Trials A4001027 and A4001028): In the majority of cases, treatment failure on maraviroc was associated with detection of CXCR4‑using virus (i.e., CXCR4- or dual/mixed‑tropic) which was not detected by the tropism assay prior to treatment. CXCR4‑using virus was detected at failure in approximately 55% of subjects who failed treatment on maraviroc by Week 48, as compared with 9% of subjects who experienced treatment failure in the placebo arm. To investigate the likely origin of the on‑treatment CXCR4‑using virus, a detailed clonal analysis was conducted on virus from 20 representative subjects (16 subjects from the maraviroc arms and 4 subjects from the placebo arm) in whom CXCR4‑using virus was detected at treatment failure. From analysis of amino acid sequence differences and phylogenetic data, it was determined that CXCR4‑using virus in these subjects emerged from a low level of pre-existing CXCR4‑using virus not detected by the tropism assay (which is population-based) prior to treatment rather than from a co-receptor switch from CCR5‑tropic virus to CXCR4‑using virus resulting from mutation in the virus.

Detection of CXCR4‑using virus prior to initiation of therapy has been associated with a reduced virological response to maraviroc. Furthermore, subjects failing twice-daily maraviroc at Week 48 with CXCR4‑using virus had a lower median increase in CD4+ cell counts from baseline (+41 cells per mm^3) than those subjects failing with CCR5‑tropic virus (+162 cells per mm^3). The median increase in CD4+ cell count in subjects failing in the placebo arm was +7 cells per mm^3.

Antiretroviral Treatment‑Naive Subjects (Trial A4001026): In a 96‑week trial of antiretroviral treatment‑naive subjects, 14% (12 of 85) who had only CCR5‑tropic virus at screening with an enhanced sensitivity tropism assay (TROFILE) and failed therapy on maraviroc had CXCR4‑using virus at the time of treatment failure. A detailed clonal analysis was conducted in 2 previously antiretroviral treatment‑naive subjects enrolled in a Phase 2a monotherapy trial who had CXCR4‑using virus detected after 10 days’ treatment with maraviroc. Consistent with the detailed clonal analysis conducted in treatment‑experienced subjects, the CXCR4‑using variants appear to emerge from outgrowth of a pre‑existing undetected CXCR4‑using virus. Screening with an enhanced sensitivity tropism assay reduced the number of maraviroc virologic failures with CXCR4- or dual/mixed‑tropic virus at failure to 12 compared with 24 when screening with the original tropism assay. All but one (11 of 12; 92%) of the maraviroc failures failing with CXCR4- or dual/mixed‑tropic virus also had genotypic and phenotypic resistance to the background drug lamivudine at failure and 33% (4 of 12) developed zidovudine-associated resistance substitutions.

Subjects who had only CCR5‑tropic virus at baseline and failed maraviroc therapy with CXCR4‑using virus had a median increase in CD4+ cell counts from baseline of +113 cells per mm^3 while those subjects failing with CCR5‑tropic virus had an increase of +135 cells per mm^3. The median increase in CD4+ cell count in subjects failing in the efavirenz arm was +95 cells per mm^3.

Antiretroviral Treatment‑Experienced Pediatric Subjects (Trial A4001031): In the Week 48 analysis of Trial A4001031 (n = 103), the mechanisms of resistance to maraviroc observed in the treatment-experienced pediatric population were similar to those observed in adult populations: reasons for virologic failure included failing with CXCR4- or dual/mixed-tropic virus, evidence of reduced maraviroc susceptibility as measured by a decrease in maximal percentage inhibition (MPI), and emergence of resistance to background drug in the regimen.

13 NONCLINICAL TOXICOLOGY

13.1 Carcinogenesis, Mutagenesis, Impairment of Fertility

Carcinogenesis

Long-term oral carcinogenicity studies of maraviroc were carried out in rasH2 transgenic mice (6 months) and in rats for up to 96 weeks (females) and 104 weeks (males). No drug-related increases in tumor incidence were found in mice at 1,500 mg per kg per day and in male and female rats at 900 mg per kg per day. The highest exposures in rats were approximately 11 times those observed in humans at the therapeutic dose of 300 mg twice daily for the treatment of HIV-1 infection.

Mutagenesis

Maraviroc was not genotoxic in the reverse mutation bacterial test (Ames test in Salmonella and E. coli), a chromosome aberration test in human lymphocytes, and mouse bone marrow micronucleus test.

Impairment of Fertility

Maraviroc did not impair mating or fertility of male or female rats and did not affect sperm of treated male rats at approximately 20-fold higher exposures (AUC) than in humans given the recommended 300-mg twice-daily dose.

14 CLINICAL STUDIES

14.1 Clinical Studies in Adult Subjects

The clinical efficacy and safety of SELZENTRY are derived from analyses of data from 3 trials in adult subjects infected with CCR5-tropic HIV-1: Trials A4001027 and A4001028 in antiretroviral treatment-experienced adult subjects and Trial A4001026 in treatment-naive subjects. These trials were supported by a 48-week trial in antiretroviral treatment-experienced adult subjects infected with dual/mixed-tropic HIV-1, Trial A4001029.

Trials in CCR5-Tropic, Treatment-Experienced Subjects

Trials A4001027 and A4001028 were double-blind, randomized, placebo-controlled, multicenter trials in subjects infected with CCR5-tropic HIV-1. Subjects were required to have an HIV-1 RNA greater than 5,000 copies per mL despite at least 6 months of prior therapy with at least 1 agent from 3 of the 4 antiretroviral drug classes (greater than or equal to 1 NRTI, greater than or equal to 1 NNRTI, greater than or equal to 2 PIs, and/or enfuvirtide) or documented resistance to at least 1 member of each class. All subjects received an optimized background regimen consisting of 3 to 6 antiretroviral agents (excluding low-dose ritonavir) selected on the basis of the subject’s prior treatment history and baseline genotypic and phenotypic viral resistance measurements. In addition to the optimized background regimen, subjects were then randomized in a 2:2:1 ratio to SELZENTRY 300 mg once daily, SELZENTRY 300 mg twice daily, or placebo. Doses were adjusted based on background therapy as described in Dosage and Administration (2), Table 1.

In the pooled analysis for Trials A4001027 and A4001028, the demographics and baseline characteristics of the treatment groups were comparable (Table 16). Of the 1,043 subjects with a CCR5-tropism result at screening, 7.6% had a dual/mixed-tropism result at the baseline visit 4 to 6 weeks later. This illustrates the background change from CCR5- to dual/mixed-tropism result over time in this treatment-experienced population, prior to a change in antiretroviral regimen or administration of a CCR5 co-receptor antagonist.

Table 16. Demographic and Baseline Characteristics of Subjects in Trials A4001027 and A4001028
 | SELZENTRY; Twice Daily; (n = 426) | Placebo; (n = 209)
Age (years)
Mean (range) | 46.3 (21-73) | 45.7 (29-72)
Sex:
Male | 382 (89.7%) | 185 (88.5%)
Female | 44 (10.3%) | 24 (11.5%)
Race:
White | 363 (85.2%) | 178 (85.2%)
Black | 51 (12.0%) | 26 (12.4%)
Other | 12 (2.8%) | 5 (2.4%)
Region:
U.S. | 276 (64.8%) | 135 (64.6%)
Non-U.S. | 150 (35.2%) | 74 (35.4%)
Subjects with previous enfuvirtide use | 142 (33.3%) | 62 (29.7%)
Subjects with enfuvirtide as part of OBT | 182 (42.7%) | 91 (43.5%)
Baseline plasma HIV-1 RNA (log10 copies/mL)
Mean (range) | 4.85 (2.96-6.88) | 4.86 (3.46-7.07)
Subjects with screening viral load >100,000 copies/mL | 179 (42.0%) | 84 (40.2%)
Baseline CD4+ cell count (cells/mm^3)
Median (range) | 167 (2-820) | 171 (1-675)
Subjects with baseline CD4+ cell count ≤200 cells/mm^3) | 250 (58.7%) | 118 (56.5%)
Subjects with Overall Susceptibility Score (OSS):a
0 | 57 (13.4%) | 35 (16.7%)
1 | 136 (31.9%) | 44 (21.1%)
2 | 104 (24.4%) | 59 (28.2%)
≥3 | 125 (29.3%) | 66 (31.6%)
Subjects with enfuvirtide resistance substitutions | 90 (21.2%) | 45 (21.5%)
Median number of resistance-associated:b
PI substitutions | 10 | 10
NNRTI substitutions | 1 | 1
NRTI substitutions | 6 | 6
NNRTI = Non-nucleoside reverse transcriptase inhibitors; NRTI = nucleoside reverse transcriptase inhibitors; OBT = optimized background therapy; PI = protease inhibitor.
a OSS - Sum of active drugs in OBT based on combined information from genotypic and phenotypic testing.
b Resistance substitutions based on IAS guidelines.^1

The Week 48 results for the pooled Trials A4001027 and A4001028 are shown in Table 17.

Table 17. Outcomes of Randomized Treatment at Week 48 in Trials A4001027 and A4001028
Outcome | SELZENTRY; Twice Daily; (n = 426) | Placebo; (n = 209) | Mean Difference
Mean change from Baseline to Week 48 in HIV-1 RNA (log10 copies/mL) | -1.84 | -0.78 | -1.05
<400 copies/mL at Week 48 | 239 (56%) | 47 (22%) | 34%
<50 copies/mL at Week 48 | 194 (46%) | 35 (17%) | 29%
Discontinuations:
Insufficient clinical response | 97 (23%) | 113 (54%) | –
Adverse events | 19 (4%) | 11 (5%) | –
Other | 27 (6%) | 18 (9%) | –
Subjects with treatment-emergent CDC Category C events | 22 (5%) | 16 (8%) | –
Deaths (during trial or within 28 days of last dose) | 9 (2%)a | 1 (0.5%) | –
a One additional subject died while receiving open-label therapy with SELZENTRY subsequent to discontinuing double-blind placebo due to insufficient response.

After 48 weeks of therapy, the proportions of subjects with HIV-1 RNA less than 400 copies per mL receiving SELZENTRY compared with placebo were 56% and 22%, respectively. The mean changes in plasma HIV-1 RNA from baseline to Week 48 were –1.84 log10 copies per mL for subjects receiving SELZENTRY + OBT compared with –0.78 log10 copies per mL for subjects receiving OBT only. The mean increase in CD4+ cell count was higher on SELZENTRY twice daily + OBT (124 cells per mm^3) than on placebo + OBT (60 cells per mm^3).

Trial in Dual/Mixed-Tropic, Treatment-Experienced Subjects

Trial A4001029 was an exploratory, randomized, double-blind, multicenter trial to determine the safety and efficacy of SELZENTRY in subjects infected with dual/mixed co-receptor tropic HIV-1. The inclusion/exclusion criteria were similar to those for Trials A4001027 and A4001028 above and the subjects were randomized in a 1:1:1 ratio to SELZENTRY once daily, SELZENTRY twice daily, or placebo. No increased risk of infection or HIV-1 disease progression was observed in the subjects who received SELZENTRY. Use of SELZENTRY was not associated with a significant decrease in HIV-1 RNA compared with placebo in these subjects and no adverse effect on CD4+ cell count was noted.

Trial in Treatment-Naive Subjects

Trial A4001026 was a randomized, double-blind, multicenter trial in subjects infected with CCR5-tropic HIV-1 classified by the original TROFILE tropism assay. Subjects were required to have plasma HIV-1 RNA greater than or equal to 2,000 copies per mL and could not have: 1) previously received any antiretroviral therapy for greater than 14 days, 2) an active or recent opportunistic infection or a suspected primary HIV-1 infection, or 3) phenotypic or genotypic resistance to zidovudine, lamivudine, or efavirenz. Subjects were randomized in a 1:1:1 ratio to SELZENTRY 300 mg once daily, SELZENTRY 300 mg twice daily, or efavirenz 600 mg once daily, each in combination with lamivudine/zidovudine. The efficacy and safety of SELZENTRY are based on the comparison of SELZENTRY twice daily versus efavirenz. In a pre-planned interim analysis at 16 weeks, SELZENTRY 300 mg once daily failed to meet the pre-specified criteria for demonstrating non-inferiority and was discontinued.

The demographic and baseline characteristics of the maraviroc and efavirenz treatment groups were comparable (Table 18). Subjects were stratified by screening HIV-1 RNA levels and by geographic region. The median CD4+ cell counts and mean HIV-1 RNA at baseline were similar for both treatment groups.

Table 18. Demographic and Baseline Characteristics of Subjects in Trial A4001026
 | SELZENTRY 300 mg Twice Daily + Lamivudine/Zidovudine; (n = 360) | Efavirenz 600 mg Once Daily + Lamivudine/Zidovudine; (n = 361)
Age (years):
Mean | 36.7 | 37.4
Range | 20-69 | 18-77
Female, n% | 104 (29) | 102 (28)
Race, n%:
White | 204 (57) | 198 (55)
Black | 123 (34) | 133 (37)
Asian | 6 (2) | 5 (1)
Other | 27 (8) | 25 (7)
Median (range) CD4+ cell count (cells/microL) | 241 (5-1,422) | 254 (8-1,053)
Median (range) HIV-1 RNA (log10 copies/mL) | 4.9 (3-7) | 4.9 (3-7)

The treatment outcomes at 96 weeks for Trial A4001026 are shown in Table 19. Treatment outcomes are based on reanalysis of the screening samples using a more sensitive tropism assay, enhanced sensitivity TROFILE HIV tropism assay, which became available after the Week 48 analysis; approximately 15% of the subjects identified as CCR5-tropic in the original analysis had dual/mixed- or CXCR4-tropic virus. Screening with enhanced sensitivity version of the TROFILE tropism assay reduced the number of maraviroc virologic failures with CXCR4- or dual/mixed-tropic virus at failure to 12 compared with 24 when screening with the original TROFILE HIV tropism assay.

Table 19. Trial Outcome (Snapshot) at Week 96 Using Enhanced Sensitivity Assaya
Outcome at Week 96b | SELZENTRY 300 mg Twice Daily + Lamivudine/Zidovudine; (n = 311); n (%) | Efavirenz 600 mg Once Daily +; Lamivudine/Zidovudine; (n = 303); n (%)
Virologic Responders:
(HIV-1 RNA <400 copies/mL) | 199 (64) | 195 (64)
Virologic Failure:
Non-sustained HIV-1 RNA suppression | 39 (13) | 22 (7)
HIV-1 RNA never suppressed | 9 (3) | 1 (<1)
Virologic Responders:
(HIV-1 RNA <50 copies/mL) | 183 (59) | 190 (63)
Virologic Failure:
Non-sustained HIV-1 RNA suppression | 43 (14) | 25 (8)
HIV-1 RNA never suppressed | 21 (7) | 3 (1)
Discontinuations due to:
Adverse events | 19 (6) | 47 (16)
Death | 2 (1) | 2 (1)
Otherc | 43 (14) | 36 (12)
a The total number of subjects (311, 303) in Table 19 represents the subjects who had a CCR5-tropic virus in the reanalysis of screening samples using the more sensitive tropism assay. This reanalysis reclassified approximately 15% of subjects shown in Table 18 as having dual/mixed- or CXCR4-tropic virus. These numbers are different than those presented in Table 18 because the numbers in Table 18 reflect the subjects with CCR5-tropic virus according to the original tropism assay.
b Week 48 results: Virologic responders (less than 400): 228 of 311 (73%) in SELZENTRY, 219 of 303 (72%) in efavirenz;
Virologic responders (less than 50): 213 of 311 (69%) in SELZENTRY, 207 of 303 (68%) in efavirenz.
c Other reasons for discontinuation include lost to follow-up, withdrawn, protocol violation, and other.

The median increase from baseline in CD4+ cell counts at Week 96 was 184 cells per mm^3 for the arm receiving SELZENTRY compared with 155 cells per mm^3 for the efavirenz arm.

14.2 Clinical Studies in Pediatric Subjects

Trial in CCR5-Tropic, Treatment-Experienced Subjects

Trial A4001031 is an open-label, multicenter trial in pediatric subjects aged 2 to less than 18 years infected with only CCR5‑tropic HIV‑1. Subjects were required to have HIV‑1 RNA greater than 1,000 copies per mL at screening. All subjects (n = 103) received SELZENTRY twice daily and OBT. Dosing of SELZENTRY was based on BSA and doses were adjusted based on whether the subject was receiving potent CYP3A inhibitors and/or inducers.

The population was 52% female and 69% black, with mean age of 10 years (range: 2 to 17 years). At baseline, mean plasma HIV-1 RNA was 4.4 log10 copies per mL (range: 2.4 to 6.2 log10 copies per mL), mean CD4+ cell count was 551 cells per mm^3 (range: 1 to 1,654 cells per mm^3), and mean CD4+ percent was 21% (range: 0% to 42%).

At 48 weeks, 48% of subjects treated with SELZENTRY and OBT achieved plasma HIV-1 RNA less than 48 copies per mL and 65% of subjects achieved plasma HIV-1 RNA less than 400 copies per mL. The mean CD4+ cell count (percent) increase from baseline to Week 48 was 247 cells per mm^3 (5%).

15 REFERENCES

1. IAS-USA Drug Resistance Mutations Figures. https://www.iasusa.org/resources/hiv-drug-resistance-mutations

16 HOW SUPPLIED/STORAGE AND HANDLING

Product: 50090-6238

NDC: 50090-6238-0 60 TABLET, FILM COATED in a BOTTLE

17 PATIENT COUNSELING INFORMATION

Advise the patient to read the FDA-approved patient labeling (Medication Guide and Instructions for Use).

Hepatotoxicity

Inform patients that hepatotoxicity, including life-threatening cases, has been reported with SELZENTRY; therefore, it is important to inform the healthcare professional if patients have underlying hepatitis B or C or elevations in liver-associated tests prior to treatment. Inform patients to stop SELZENTRY and seek medical evaluation immediately if they develop signs or symptoms of hepatitis or allergic reaction following use of SELZENTRY. Advise patients that laboratory tests for liver enzymes and bilirubin will be ordered prior to starting SELZENTRY, at other times during treatment, and if they develop severe rash or signs and symptoms of hepatitis or an allergic reaction on treatment [see Dosage and Administration (2.1), Warnings and Precautions (5.1, 5.2)].

Cardiovascular Events

When administering SELZENTRY in patients with cardiovascular comorbidities, a history of postural hypotension or receiving concomitant medication known to lower blood pressure, advise patients that they may be at increased risk for cardiovascular events. Advise patients to avoid driving or operating machinery if they experience dizziness while taking SELZENTRY [see Warnings and Precautions (5.3)].

Drug Interactions

Advise patients to inform their healthcare provider of concomitant HIV medications as dosage of SELZENTRY may be modified depending on other HIV medications taken with SELZENTRY. Advise patients that coadministration of SELZENTRY with St. John’s wort is not recommended as it can lead to loss of virologic response and possible resistance to SELZENTRY [see Dosage and Administration (2.2), Drug Interactions (7.1)].

Missed Dosage

Inform patients that it is important to take SELZENTRY in combination with other antiretroviral medications on a regular dosing schedule with or without food. Advise patients to avoid missing doses as it can result in development of resistance. Instruct patients that if they miss a dose, to take it as soon as they remember. Advise patients not to double their next dose or take more than the prescribed dose [see Dosage and Administration (2.2)].

Pregnancy

Inform patients that there is insufficient data on the safety of SELZENTRY in pregnancy. Inform patients that there is an antiretroviral pregnancy registry that monitors pregnancy outcomes in women exposed to SELZENTRY during pregnancy [see Use in Specific Populations (8.1)].

Lactation

Instruct women with HIV-1 infection not to breastfeed because HIV-1 can be passed to the baby in breast milk [see Use in Specific Populations (8.2)].

SELZENTRY and COMBIVIR are trademarks owned by or licensed to the ViiV Healthcare group of companies.

TROFILE is a trademark owned by or licensed to Monogram BioSciences, Inc., and is not owned by or licensed to the ViiV Healthcare group of companies. The maker of this brand is not affiliated with and does not endorse the ViiV Healthcare group of companies or its products.

Manufactured for:

ViiV Healthcare

Durham, NC 27701

©2022 ViiV Healthcare group of companies or its licensor.

SEL:16PI

PHARMACIST‑DETACH HERE AND GIVE MEDICATION GUIDE TO PATIENT

_ _ _ _ _ _ _ _ _ _ _ _ _ _ _ _ _ _ _ _ _ _ _ _ _ _ _ _ _ _ _ _ _ _ _ _ _ _ _ _ _ _ _ _ _ _ _ _ _ _ _ _ _

MEDICATION GUIDE

SELZENTRY (sell-ZEN-tree)

(maraviroc)

tablets

SELZENTRY (sell-ZEN-tree)

(maraviroc)

oral solution

What is the most important information I should know about SELZENTRY?

SELZENTRY can cause serious side effects including serious liver problems (liver toxicity). Some people who take SELZENTRY can develop a severe rash or an allergic reaction before liver problems happen and may be life-threatening. Stop taking SELZENTRY and call your healthcare provider right away if you get any of the following signs or symptoms of liver problems:

- an itchy rash on your body (allergic reaction)
- your skin or the white part of your eyes turns yellow (jaundice)
- dark or “tea-colored” urine

- vomiting
- pain, aching, or tenderness on the right side of your stomach area

Your healthcare provider will do blood tests to check your liver before you begin treatment with SELZENTRY and as needed during treatment with SELZENTRY.

What is SELZENTRY?

SELZENTRY is a prescription Human Immunodeficiency Virus-1 (HIV-1) medicine given with other HIV-1 medicines to treat CCR5-tropic HIV-1 infection in adults and children weighing at least 4.4 lb (2 kg).

HIV-1 is the virus that causes Acquired Immune Deficiency Syndrome (AIDS).

Use of SELZENTRY is not recommended in people with dual/mixed- or CXCR4‑tropic HIV‑1.

SELZENTRY should not be used in premature newborns or children weighing less than 4.4 pounds (2 kg).

Do not take SELZENTRY if you have severe kidney problems or are on hemodialysis and are also taking certain other medications.

Before you take SELZENTRY, tell your healthcare provider about all of your medical conditions, including if you:

- have or have had liver problems including hepatitis B or C virus infection.
- have heart problems.
- have kidney problems.
- have low blood pressure or take medicines to lower blood pressure.
- are pregnant or plan to become pregnant. It is not known if SELZENTRY may harm your unborn baby.
  Pregnancy Registry. There is a pregnancy registry for women who take SELZENTRY during pregnancy. The purpose of this registry is to collect information about the health of you and your baby. Talk to your healthcare provider about how you can take part in this registry.
- are breastfeeding or plan to breastfeed. Do not breastfeed if you take SELZENTRY. You should not breastfeed if you have HIV-1 because of the risk of passing HIV-1 to your baby. Talk to your healthcare provider about the best way to feed your baby.

Tell your healthcare provider about all the medicines you take, including prescription and over-the-counter medicines, vitamins, and herbal supplements.

- Some medicines may interact with SELZENTRY. Keep a list of your medicines to show your healthcare provider and pharmacist.
- You can ask your healthcare provider or pharmacist for a list of medicines that interact with SELZENTRY.

Do not start taking a new medicine without telling your healthcare provider. Your healthcare provider can tell you if it is safe to take SELZENTRY with other medicines. Your healthcare provider may need to change your dose of SELZENTRY when you take it with certain medicines. You should not take SELZENTRY if you also take St. John’s wort (Hypericum perforatum).

How should I take SELZENTRY?

- Take SELZENTRY exactly as your healthcare provider tells you.
- Do not change your dose or stop taking SELZENTRY without first talking with your healthcare provider.
- If you miss a dose of SELZENTRY, take it as soon as you remember. Do not take 2 doses at the same time. If you are not sure about your dosing, call your healthcare provider.
- Stay under the care of a healthcare provider during treatment with SELZENTRY.
- Swallow SELZENTRY tablets whole. Do not chew the tablets.
- SELZENTRY may be taken with or without food.
- Your healthcare provider will prescribe a dose of SELZENTRY based on your child’s body weight and other medicines they are taking.
- Tell your healthcare provider if your child has trouble swallowing tablets. SELZENTRY comes as tablets or as a liquid (oral solution).
- SELZENTRY oral solution should be given with the supplied press-in bottle adapter and oral dosing syringe. See the Instructions for Use that comes with SELZENTRY oral solution for information about the right way to take a dose.
- Do not run out of SELZENTRY. The virus in your blood may increase and the virus in your blood may become harder to treat. When your supply starts to run low, get more from your healthcare provider or pharmacy.
- If you take too much SELZENTRY, call your healthcare provider or go to the nearest hospital emergency room right away.

What are the possible side effects of SELZENTRY?

SELZENTRY can cause serious side effects including:

- See “What is the most important information I should know about SELZENTRY?”
- Severe skin rash and allergic reactions. Severe and potentially life-threatening skin reactions and allergic reactions have been reported in some people taking SELZENTRY. If you develop a rash with any of the following symptoms, stop using SELZENTRY and contact your healthcare provider right away:

- fever
- generally ill feeling
- muscle aches
- blisters or sores in your mouth
- blisters or peeling of the skin
- redness or swelling of the eyes
- swelling of the mouth or face or lips

- problems breathing
- yellowing of the skin or whites of your eyes
- dark or tea-colored urine
- pain, aching, or tenderness on the right side below the ribs
- loss of appetite
- nausea/vomiting

- Heart problems including heart attack.
- Low blood pressure when standing up (postural hypotension) that can cause dizziness or fainting. You should avoid driving or operating heavy machinery if you have dizziness during treatment with SELZENTRY.
- Changes in your immune system (Immune Reconstitution Syndrome) can happen when you start taking HIV-1 medicines. Your immune system may get stronger and begin to fight infections that have been hidden in your body for a long time. Tell your healthcare provider right away if you develop new symptoms during treatment with SELZENTRY.
- Possible chance of infection or cancer. SELZENTRY affects other immune system cells and therefore may possibly increase your chance for getting other infections or cancer.

The most common side effects of SELZENTRY in adults include colds and cold-like symptoms, cough, fever, rash, bloating and gas, indigestion, constipation, and dizziness.

The most common side effects of SELZENTRY in children include vomiting, abdominal pain, diarrhea, nausea, and dizziness.

The most common side effect of SELZENTRY in newborns is decreased hemoglobin (protein inside red blood cells).

These are not all the possible side effects of SELZENTRY. Call your doctor for medical advice about side effects. You may report side effects to FDA at 1‑800‑FDA‑1088.

How should I store SELZENTRY?

- Store SELZENTRY tablets and oral solution at room temperature between 68°F to 77°F (20°C to 25°C).
- Throw away any unused oral solution 60 days after first opening the bottle.

Keep SELZENTRY and all medicines out of the reach of children.

General information about the safe and effective use of SELZENTRY

Medicines are sometimes prescribed for purposes other than those mentioned in a Medication Guide. Do not use SELZENTRY for a condition for which it was not prescribed. Do not give SELZENTRY to other people, even if they have the same symptoms that you have. It may harm them.

You can ask your pharmacist or healthcare provider for the information about SELZENTRY that is written for health professionals.

What are the ingredients in SELZENTRY?

Active ingredient: maraviroc

Inactive ingredients:

Tablets: Dibasic calcium phosphate (anhydrous), magnesium stearate, microcrystalline cellulose, and sodium starch glycolate. Tablet film-coating contains: FD&C blue #2 aluminum lake, soya lecithin, polyethylene glycol (macrogol 3350), polyvinyl alcohol, talc, and titanium dioxide.

Oral Solution: Citric acid, purified water, sodium benzoate, sodium citrate dihydrate, strawberry flavoring (501440T), and sucralose.

Manufactured for:

ViiV Healthcare

Durham, NC 27701

SELZENTRY is a trademark owned by or licensed to the ViiV Healthcare group of companies.

©2022 ViiV Healthcare group of companies or its licensor.

SEL:10MG

For more information go to www.selzentry.com.

This Medication Guide has been approved by the U.S. Food and Drug Administration.

Revised: 9/2022

INSTRUCTIONS FOR USE

SELZENTRY (sell-ZEN-tree)

(maraviroc)

oral solution

Read this Instructions for Use before you start taking SELZENTRY oral solution and each time you get a refill. There may be new information. This leaflet does not take the place of talking to your healthcare provider about your medical condition or treatment.

Important information about measuring SELZENTRY oral solution:

Always use the correct oral syringe that comes with your SELZENTRY oral solution to measure your prescribed dose. Ask your healthcare provider or pharmacist to show you which syringe to use and how to measure your prescribed dose if you are not sure.

Each carton of SELZENTRY oral solution contains:

- One 3-mL oral syringe (for doses of 2.5 mL or less)
- One 10-mL oral syringe (for doses more than 2.5 mL)
- 1 press-in bottle adapter
- 1 bottle of SELZENTRY oral solution

Before each use: Wash your hands with soap and water. Place the items from the carton on a clean flat surface.
Step 1. Open the bottle of SELZENTRY oral solution.
Open the bottle by pushing down firmly on the child-resistant cap and turning it counter-clockwise. See Figure A.

Do not throw away the child-resistant cap.

Figure A. Opening the bottle

Step 2. First time use only: Insert the press-in bottle adapter.
Remove the press-in bottle adapter and oral syringe from the plastic overwrap. With the bottle on a flat surface, push the ribbed end of the press-in bottle adapter all the way into the neck of the bottle while holding the bottle firmly. See Figure B.

Note: Do not remove the press-in bottle adapter from the bottle after it is inserted.

Figure B. Inserting the press-in bottle adapter

Step 3. Choose the oral syringe you need and find your prescribed dose on the oral syringe.
Check the dose in milliliters (mL) as prescribed by your healthcare provider. Choose the right syringe for your child’s dose: use the 3-mL (small) syringe for doses of 2.5 mL or less, or the 10-mL (large) syringe for doses more than 2.5 mL. Then find this marking on the oral syringe. See Figure C.

Figure C. Choose the oral syringe you need and find your prescribed dose.

Step 4. Remove air from oral syringe.
Push the oral syringe plunger to the bottom of the barrel of the syringe (toward its tip) to remove excess air. See Figure D.

Figure D. Removing air from oral syringe.

Step 5. Insert the oral syringe.
Insert the oral syringe into the upright bottle through the opening of the press-in bottle adapter until it is firmly in place. See Figure E.

Figure E. Inserting the oral syringe

Step 6. Withdraw the prescribed dose of SELZENTRY from the bottle.
With the oral syringe in place, turn the bottle upside down. Pull back the plunger of the oral syringe until the top of the plunger is even with the markings on the oral syringe for your prescribed dose. See Figure F.

If you see air bubbles in the oral syringe, fully push the plunger in to empty the oral solution back into the bottle. Then withdraw your prescribed dose of oral solution.

Figure F. Withdrawing the oral solution

Step 7. Removing the oral syringe.
Turn the bottle upright and place the bottle on a flat surface. Remove the oral syringe from the bottle adapter and bottle by pulling straight up on the barrel of the oral syringe. See Figure G.

Figure G. Removing the oral syringe

Step 8. Check the dose withdrawn.
Check that the correct dose was drawn up into the oral syringe. See Figure H.

If the dose is not correct, re-insert the oral syringe tip firmly into the bottle adapter. Fully push in the plunger so that the oral solution flows back into the bottle. Repeat Steps 6 and 7.

Figure H. Checking the dose withdrawn.

Step 9. Take the dose of SELZENTRY. See Figure I.
Place the tip of the oral syringe against the inside of the child’s cheek.

Slowly push the plunger all the way down to give all the medicine in the oral syringe. Make sure the child has time to swallow the medicine.

Note: If the prescribed dose is more than 10 mL, you will need to divide the dose. Follow the instructions given to you by your healthcare provider or pharmacist about how to divide the dose and repeat Steps 5 through 9.

Figure I. Taking the dose of SELZENTRY

Step 10. Close the bottle.
Close the bottle tightly by turning the child-resistant cap clockwise, leaving the press-in bottle adapter in place. See Figure J.

Figure J. Closing the bottle

Step 11. Clean the oral syringe.
Rinse the oral syringe with tap water after each use.

Remove the plunger from the barrel by pulling the plunger and the barrel away from each other. See Figure K.

Rinse the plunger and barrel with water. See Figure L.

Allow parts to air dry completely.

Figure K. Removing the plunger from the barrel

Figure L. Rinsing the plunger and barrel

Step 12. Put the oral syringe back together.
When the barrel and plunger are dry, put the oral syringe back together by inserting the plunger into the barrel. See Figure M. Store the oral syringe with the SELZENTRY oral solution.

Do not throw away the oral syringe.

Figure M. Putting the oral syringe back together

How should I store SELZENTRY?

Store SELZENTRY oral solution at room temperature between 68°F to 77°F (20°C to 25°C).

- Throw away any unused oral solution 60 days after first opening the bottle.

Ask your healthcare provider or pharmacist how to dispose of unused oral solution.

Keep SELZENTRY and all medicines out of the reach of children.

Manufactured for:

ViiV Healthcare

Durham, NC 27701

SELZENTRY is a trademark owned by or licensed to the ViiV Healthcare group of companies.

©2022 ViiV Healthcare group of companies or its licensor.

SEL:4IFU

This Instructions for Use has been approved by the U.S. Food and Drug Administration.

Revised: 9/2022